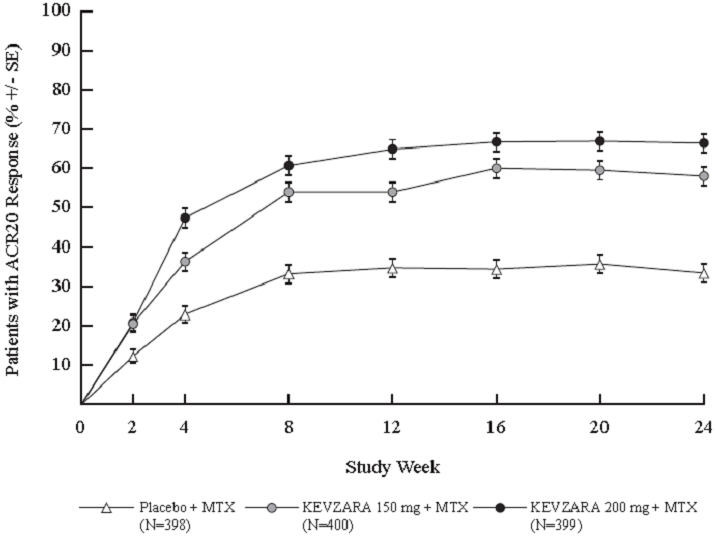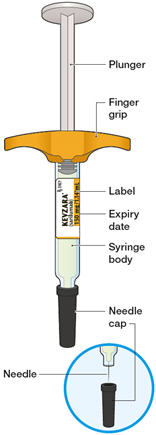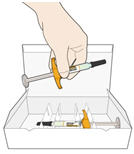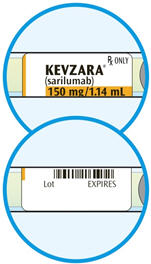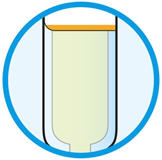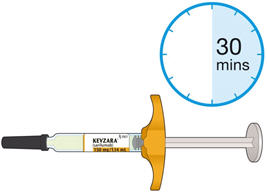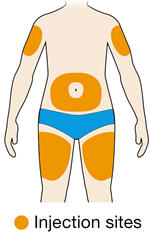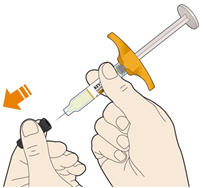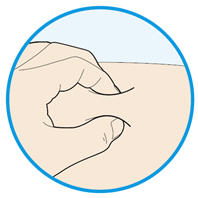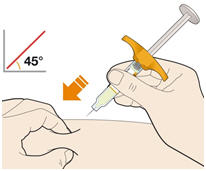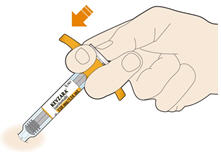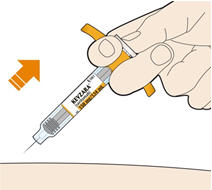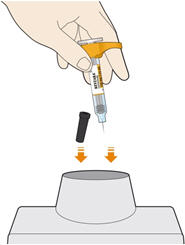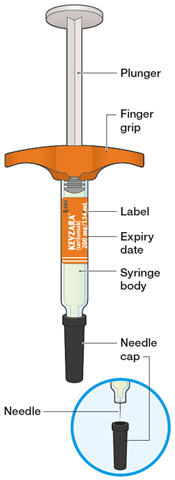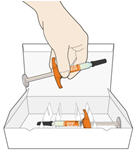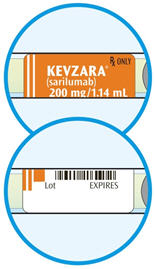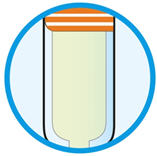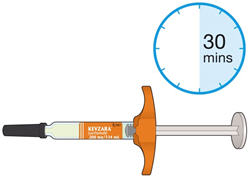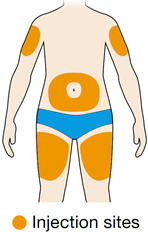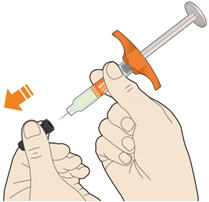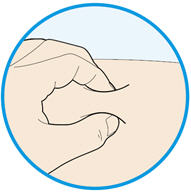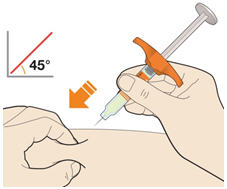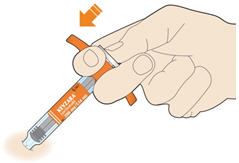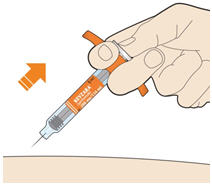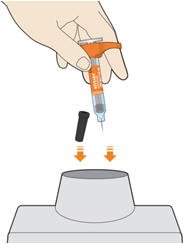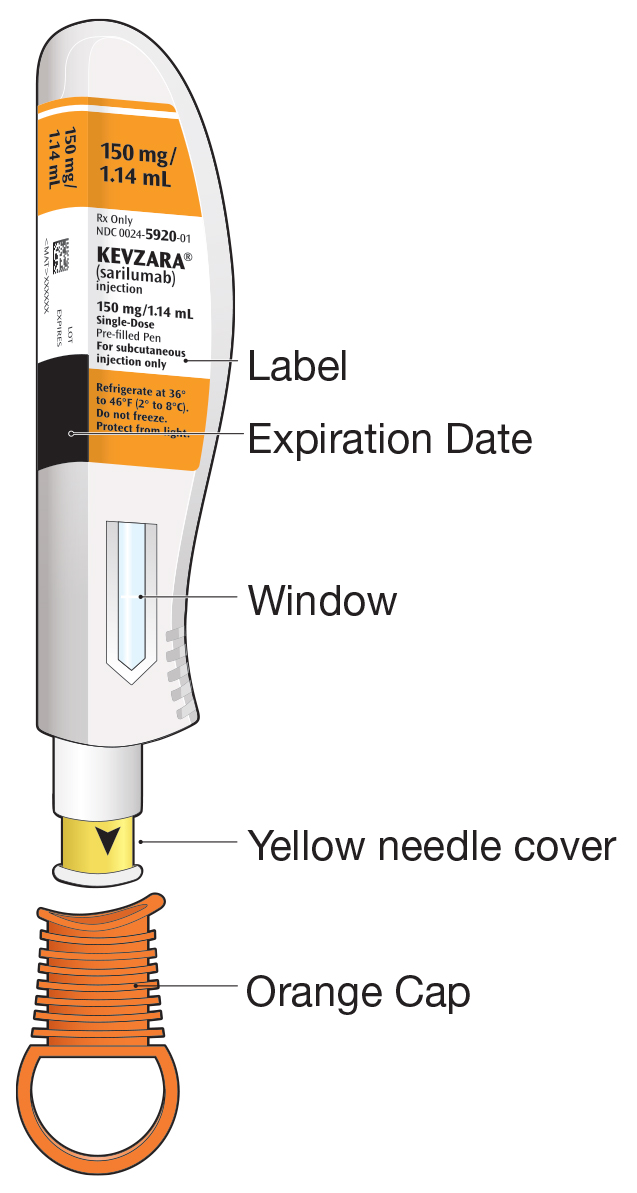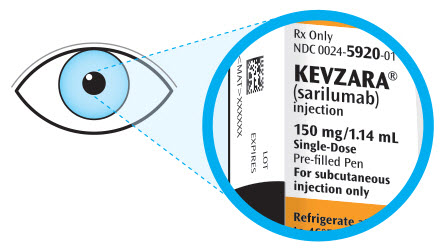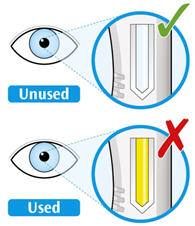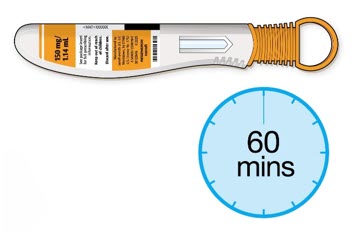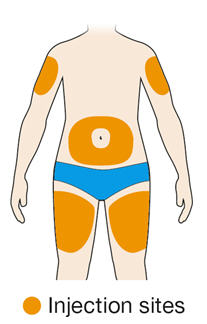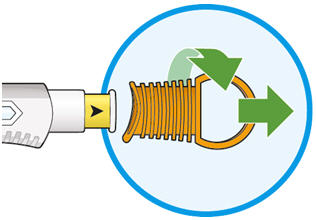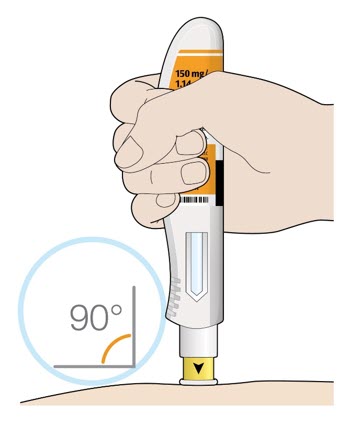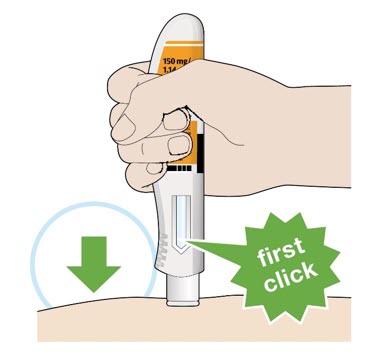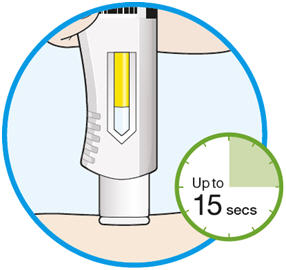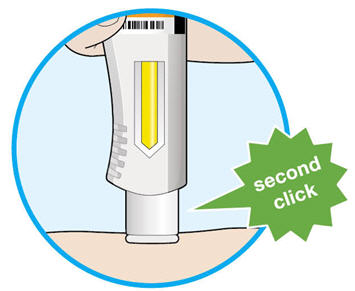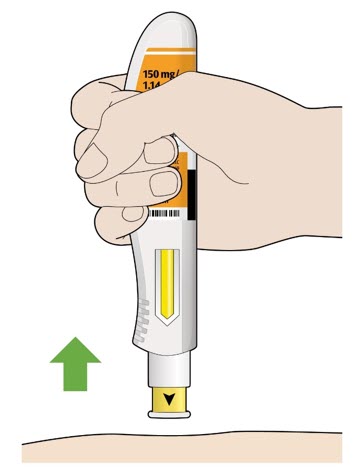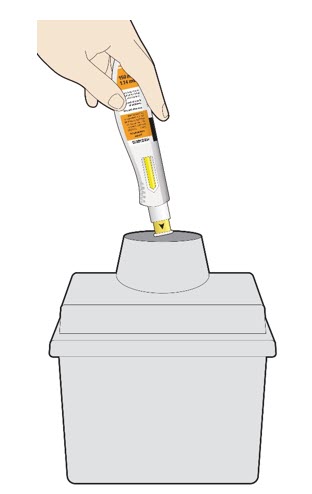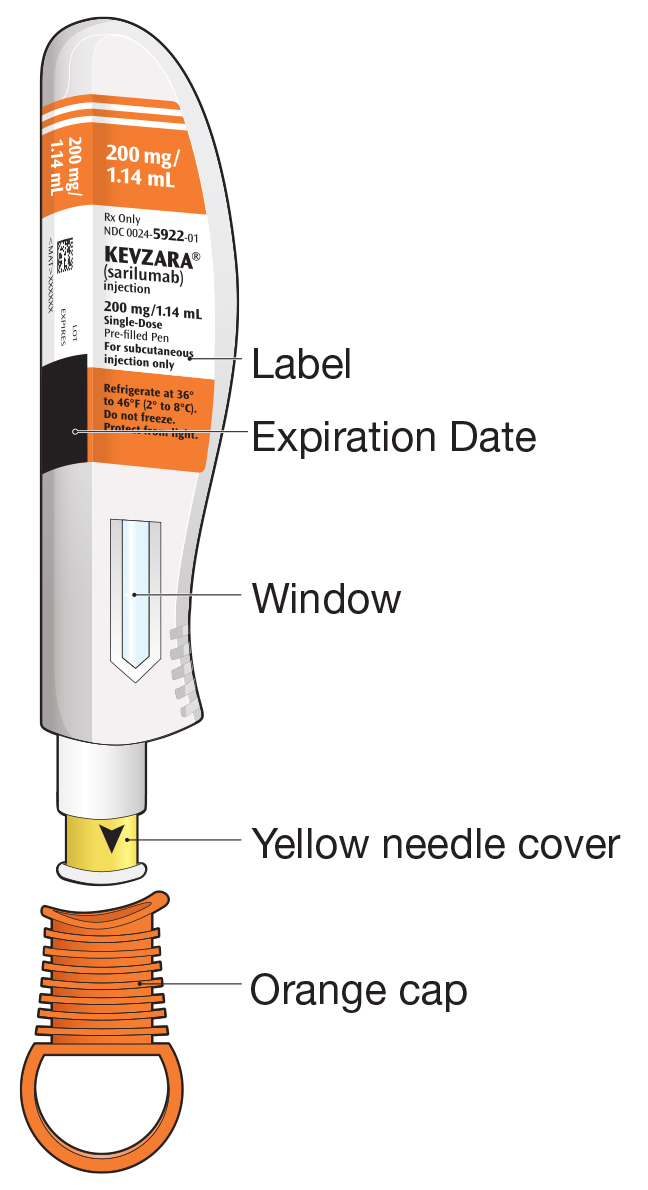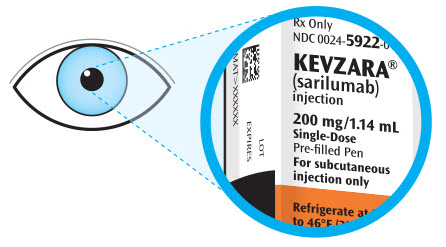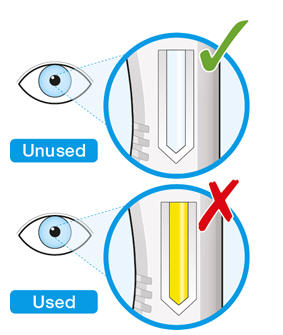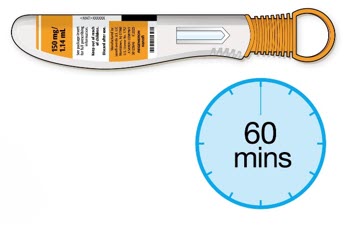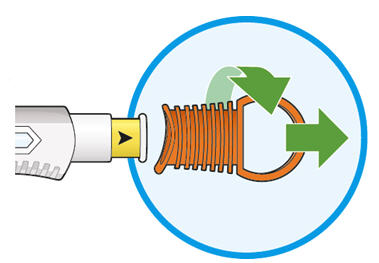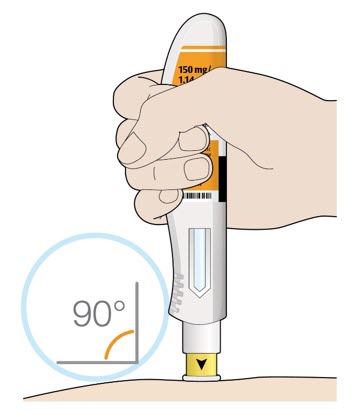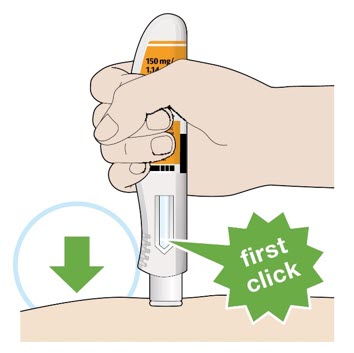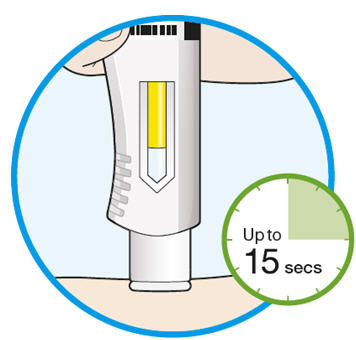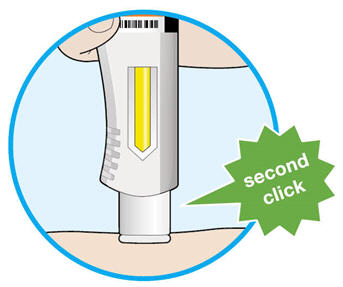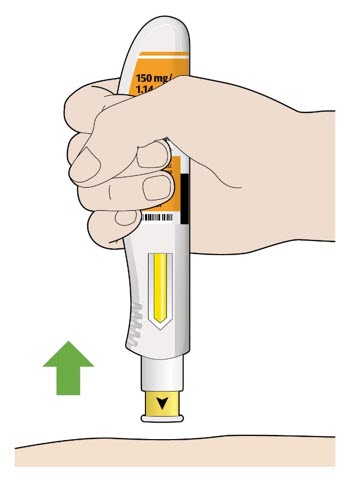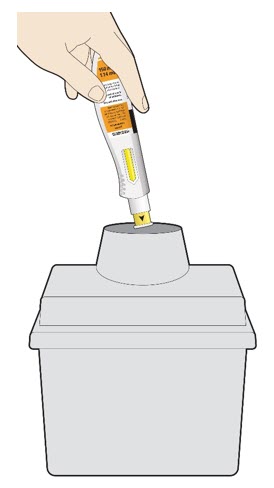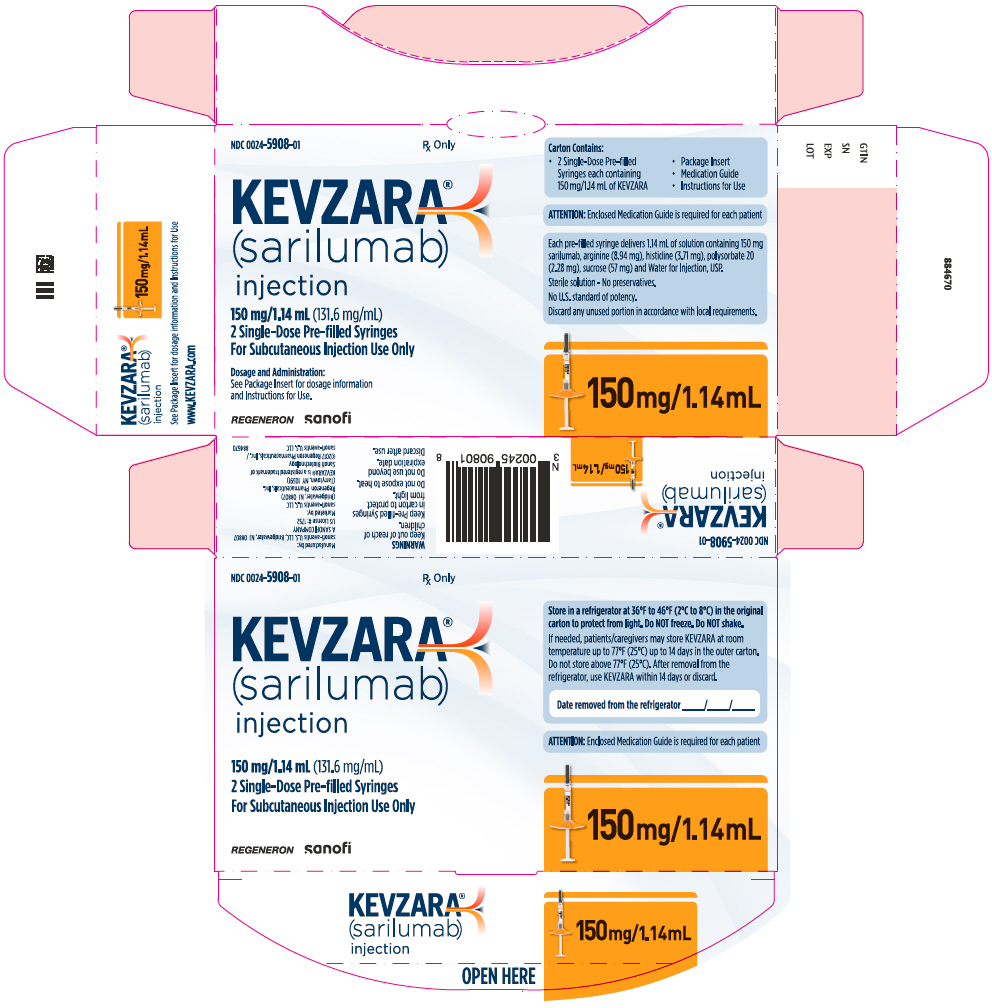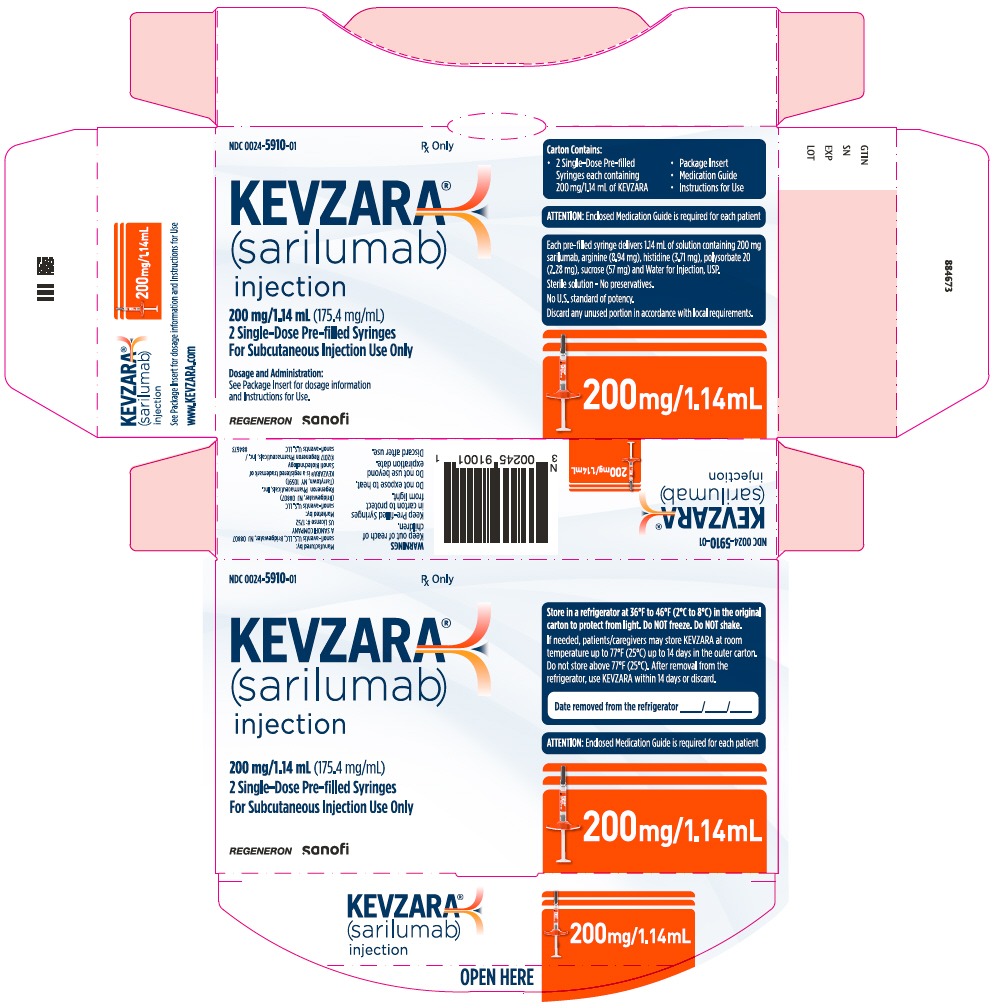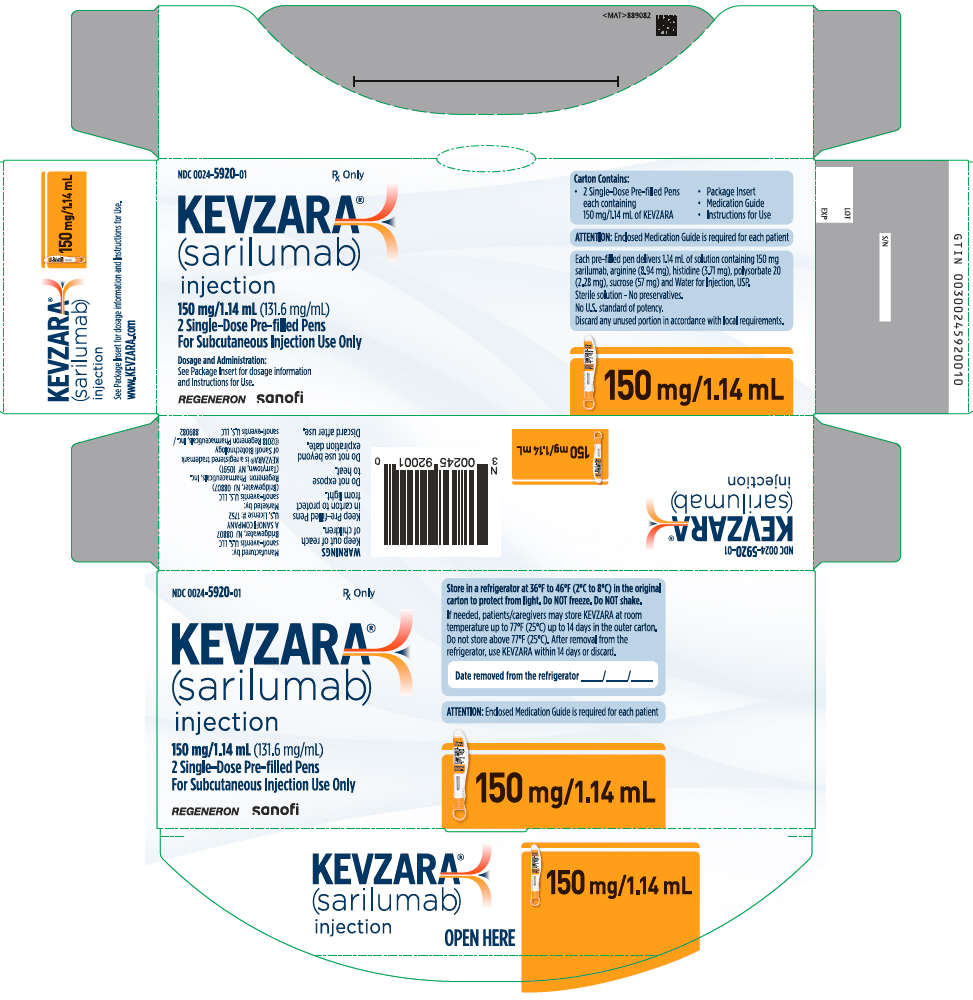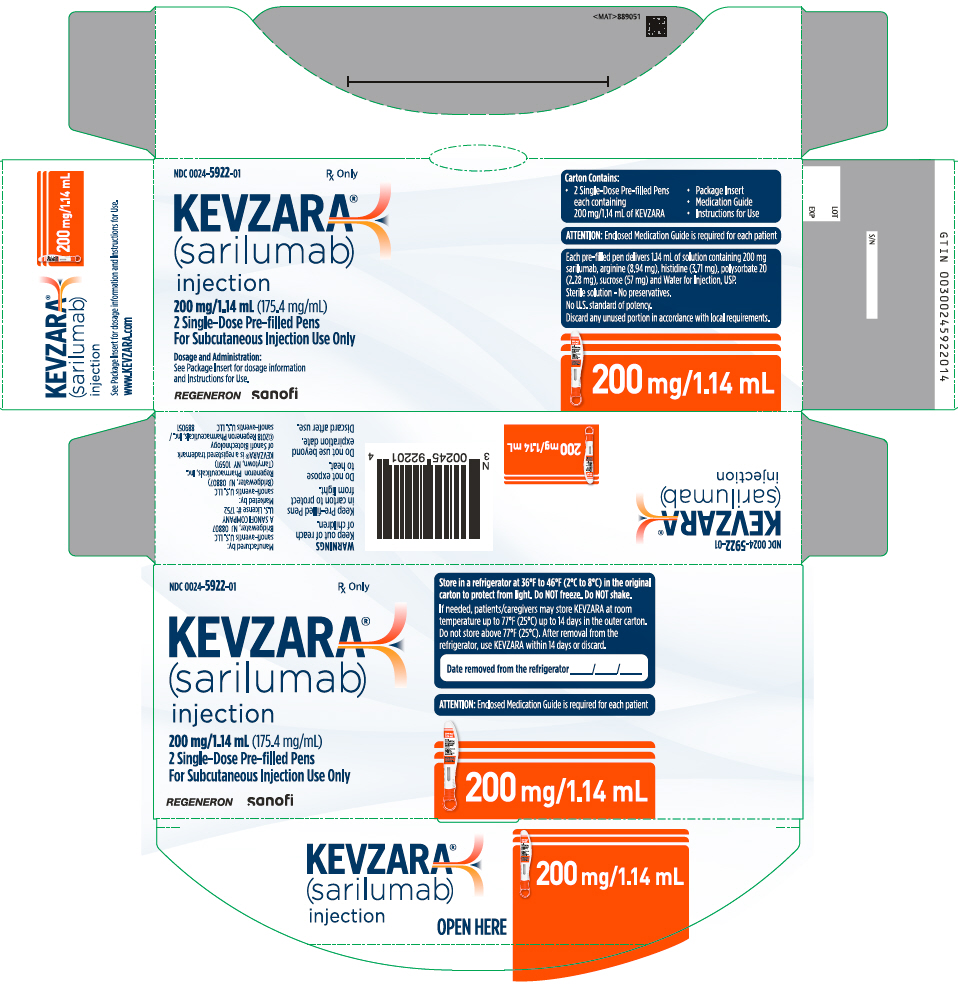 DRUG LABEL: KEVZARA
NDC: 0024-5908 | Form: INJECTION, SOLUTION
Manufacturer: Sanofi-Aventis U.S. LLC
Category: prescription | Type: HUMAN PRESCRIPTION DRUG LABEL
Date: 20250516

ACTIVE INGREDIENTS: SARILUMAB 150 mg/1.14 mL
INACTIVE INGREDIENTS: ARGININE 8.94 mg/1.14 mL; HISTIDINE 3.71 mg/1.14 mL; POLYSORBATE 20 2.28 mg/1.14 mL; SUCROSE 57 mg/1.14 mL; WATER

HIGHLIGHTS OF PRESCRIBING INFORMATION

These highlights do not include all the information needed to use KEVZARA® safely and effectively. See full prescribing information for KEVZARA.
KEVZARA (sarilumab) injection, for subcutaneous use
Initial U.S. Approval: 2017

WARNING: RISK OF SERIOUS INFECTIONS

See full prescribing information for complete boxed warning.

- Serious infections leading to hospitalization or death including bacterial, viral, invasive fungal, and other opportunistic infections have occurred in patients receiving KEVZARA. (5.1)
- If a serious infection develops, interrupt KEVZARA until the infection is controlled. (5.1)
- Cases of tuberculosis (TB) have been reported. Prior to starting KEVZARA, test for latent TB; if positive, start treatment for TB. (5.1)
- Closely monitor patients for signs and symptoms of infection during treatment with KEVZARA. (5.1)

RECENT MAJOR CHANGES

Indications and Usage (1) | 6/2024
Dosage and Administration (2) | 6/2024

1 INDICATIONS AND USAGE

KEVZARA® is an interleukin-6 (IL-6) receptor antagonist indicated for treatment of:

- adult patients with moderately to severely active rheumatoid arthritis (RA) who have had an inadequate response or intolerance to one or more disease-modifying antirheumatic drugs (DMARDs). (1.1)
- adult patients with polymyalgia rheumatica (PMR) who have had an inadequate response to corticosteroids or who cannot tolerate corticosteroid taper. (1.2)
- patients who weigh 63 kg or greater with active polyarticular juvenile idiopathic arthritis (pJIA). (1.3)

2 DOSAGE AND ADMINISTRATION

General Considerations for Administration

- KEVZARA initiation is not recommended in patients with ANC less than 2,000/mm^3, platelets less than 150,000/mm^3 or liver transaminases above 1.5 times ULN. See Full Prescribing Information (FPI) for complete information. (2.1)

Recommended Dosage in RA

- The recommended dosage is 200 mg subcutaneously, once every 2 weeks. (2.2)
- For RA, KEVZARA may be used as monotherapy or in combination with methotrexate (MTX) or other conventional DMARDs. (2.2)

Recommended Dosage in PMR

- The recommended dosage is 200 mg subcutaneously, once every two weeks in combination with a tapering course of corticosteroids. (2.3)
- For PMR, KEVZARA can be used as monotherapy following discontinuation of corticosteroids. (2.3)

Recommended Dosage in pJIA

- The recommended dosage is 200 mg given subcutaneously once every 2 weeks for pJIA patients who weigh 63 kg or greater using the 200 mg/1.14 mL pre-filled syringe. (2.4)
- For pJIA, KEVZARA can be used as monotherapy or in combination with conventional DMARDs. (2.4)

Dosage Modifications for Cytopenias, Abnormal Liver Enzymes, Infections

- See FPI for complete information. (2.6)

3 DOSAGE FORMS AND STRENGTHS

- Injection: 150 mg/1.14 mL and 200 mg/1.14 mL solution in a single-dose pre-filled syringe (3)
- Injection: 150 mg/1.14 mL and 200 mg/1.14 mL solution in a single-dose pre-filled pen (3)

4 CONTRAINDICATIONS

KEVZARA is contraindicated in patients with known hypersensitivity to sarilumab or any of the inactive ingredients. (4)

5 WARNINGS AND PRECAUTIONS

- Serious Infections: Avoid KEVZARA use during an active infection. (5.1)
- Neutropenia, Thrombocytopenia, Elevated Liver Enzymes, Lipid Abnormalities: Monitor laboratory parameters. (5.2)
- Gastrointestinal (GI) Perforation: Risk may be increased with concurrent diverticulitis or concomitant use of NSAIDs or corticosteroids. Promptly evaluate acute abdominal signs or symptoms. (5.3)
- Hypersensitivity reactions. (5.5)
- Live vaccines: Avoid use with KEVZARA. (5.7, 7.3)

6 ADVERSE REACTIONS

Most common adverse reactions are:

- Rheumatoid Arthritis (incidence ≥3 %): neutropenia, increased ALT, injection site erythema, upper respiratory infections and urinary tract infections. (6.1)
- Polymyalgia Rheumatica (incidence ≥ 5%): neutropenia, leukopenia and injection site pruritus. (6.1)
- Polyarticular Juvenile Idiopathic Arthritis: nasopharyngitis, neutropenia, upper respiratory tract infection and injection site erythema. (6.1)

To report SUSPECTED ADVERSE REACTIONS, contact sanofi-aventis at 1-800-633-1610 or FDA at 1-800-FDA-1088 or www.fda.gov/medwatch

8 USE IN SPECIFIC POPULATIONS

- Lactation: Discontinue drug or nursing taking into consideration importance of drug to mother. (8.2)

FULL PRESCRIBING INFORMATION

WARNING: RISK OF SERIOUS INFECTIONS

Patients treated with KEVZARA are at increased risk for developing serious infections that may lead to hospitalization or death [see Warnings and Precautions (5.1), Adverse Reactions (6.1)]. Opportunistic infections have also been reported in patients receiving KEVZARA. Most patients who developed infections were taking concomitant immunosuppressants such as methotrexate or corticosteroids.

Avoid use of KEVZARA in patients with an active infection.

Reported infections include:

- Active tuberculosis, which may present with pulmonary or extrapulmonary disease. Patients should be tested for latent tuberculosis before KEVZARA use and during therapy. Treatment for latent infection should be initiated prior to KEVZARA use.
- Invasive fungal infections, such as candidiasis, and pneumocystis. Patients with invasive fungal infections may present with disseminated, rather than localized, disease.
- Bacterial, viral and other infections due to opportunistic pathogens.

Closely monitor patients for signs and symptoms of infection during treatment with KEVZARA. If a serious infection develops, interrupt KEVZARA until the infection is controlled.

Consider the risks and benefits of treatment with KEVZARA prior to initiating therapy in patients with chronic or recurrent infection.

1 INDICATIONS AND USAGE

1.1 Rheumatoid Arthritis (RA)

KEVZARA® is indicated for treatment of adult patients with moderately to severely active rheumatoid arthritis who have had an inadequate response or intolerance to one or more disease-modifying antirheumatic drugs (DMARDs).

1.2 Polymyalgia Rheumatica (PMR)

KEVZARA is indicated for treatment of adult patients with polymyalgia rheumatica who have had an inadequate response to corticosteroids or who cannot tolerate corticosteroid taper.

1.3 Polyarticular Juvenile Idiopathic Arthritis (pJIA)

KEVZARA is indicated for treatment of active polyarticular juvenile idiopathic arthritis (pJIA) in patients who weigh 63 kg or greater.

2 DOSAGE AND ADMINISTRATION

2.1 General Considerations Prior to Administration

Not Recommended for Concomitant Use with Biological DMARDS

The concurrent use of KEVZARA with biological DMARDs such as tumor necrosis factor (TNF) antagonists, IL-1R antagonists, anti-CD20 monoclonal antibodies and selective co-stimulation modulators has not been studied. Avoid using KEVZARA with biological DMARDs because of the possibility of increased immunosuppression and increased risk of infection.

Recommended Evaluations Prior to Treatment

- Complete blood count (CBC): Treatment initiation with KEVZARA is not recommended in patients with an absolute neutrophil count (ANC) below 2000 per mm^3, or platelet count below 150,000 per mm^3. Monitor laboratory parameters [see Warnings and Precautions (5.2)].
- Liver function tests (LFT): Treatment initiation with KEVZARA is not recommended in patients with or who have alanine transaminase (ALT) or aspartate aminotransferase (AST) above 1.5 times the upper limit of normal (ULN). Monitor laboratory parameters [see Dosage and Administration (2.6) and Warnings and Precautions (5.2)].
- Lipid parameters (total cholesterol, LDL cholesterol, HDL cholesterol and/or triglycerides): Assess lipid parameters at baseline. Monitor laboratory parameters [see Warnings and Precautions (5.2)].
- Active and latent tuberculosis infection evaluation: Prior to initiating KEVZARA, test patients for active and latent tuberculosis (TB). KEVZARA should not be administered to patients with active TB. If positive for latent infection, consider treating for TB prior to KEVZARA use [see Warnings and Precautions (5.1)].
- Evaluate for infections: Avoid KEVZARA use in patients with active infections [see Warnings and Precautions (5.1)].

2.2 Recommended Dosage for Rheumatoid Arthritis

The recommended dosage of KEVZARA is 200 mg once every two weeks given as a subcutaneous injection [see Dosage and Administration (2.1)].

KEVZARA may be used as monotherapy or in combination with methotrexate (MTX) or other conventional DMARDs.

Modify the dosage as recommended in Table 1 if the patient develops neutropenia, thrombocytopenia, or liver enzyme abnormalities [see Dosage and Administration (2.6), Warnings and Precautions (5.2) and Adverse Reactions (6.1)].

2.3 Recommended Dosage for Polymyalgia Rheumatica

The recommended dosage of KEVZARA is 200 mg once every two weeks given as a subcutaneous injection, in combination with a tapering course of systemic corticosteroids [see Dosage and Administration (2.1)]. KEVZARA can be used as monotherapy following discontinuation of corticosteroids.

Discontinue KEVZARA if the patient develops neutropenia (using ANC results obtained at the end of the dosing interval), thrombocytopenia, or liver enzyme abnormalities [see Dosage and Administration (2.6), Warnings and Precautions (5.2) and Adverse Reactions (6.1)].

2.4 Recommended Dosage for Polyarticular Juvenile Idiopathic Arthritis

The recommended dosage of KEVZARA for patients who weigh 63 kg and greater is 200 mg once every two weeks given as a subcutaneous injection (maximum dose 200 mg). Dosage in this patient population can be achieved by administering the 200 mg/1.14 mL pre-filled syringe. The pre-filled pen is not intended for use in pediatric patients [see Dosage and Administration (2.6), Warnings and Precautions (5.2) and Adverse Reactions (6.1)]. KEVZARA is not approved in pediatric patients weighing less than 63 kg because of the lack of an appropriate dosage form.

In patients with pJIA, KEVZARA can be used alone or in combination with conventional DMARDs.

2.5 Preparation and Administration Instructions

Parenteral drug products should be inspected visually for particulate matter and discoloration prior to administration. KEVZARA solution should be clear and colorless to pale yellow. Do not use if the solution is cloudy, discolored or contains particles, or if any part of the pre-filled syringe or pre-filled pen appears to be damaged.

Rotate injection sites with each injection. Do not inject into skin that is tender, damaged, or has bruises or scars.

Pre-filled Pen and Pre-filled Syringe

- KEVZARA is intended for use under the guidance of a healthcare professional. A patient may self-inject KEVZARA or the patient's caregiver may administer KEVZARA. Provide proper training to patients and/or caregivers on the preparation and administration of KEVZARA prior to use according to the Instructions for Use (IFU).
- Allow the pre-filled syringe to sit at room temperature for 30 minutes prior to subcutaneous injection. Do not warm KEVZARA in any other way.
- If using a pre-filled pen, allow the pre-filled pen to sit at room temperature for 60 minutes prior to subcutaneous injection. Do not warm KEVZARA in any other way.
- Instruct patients to inject the full amount in the syringe or pen (1.14 mL), which provides 200 mg or 150 mg of KEVZARA, according to the directions provided in the IFU.
- The ability of pediatric patients to self-inject with the pre-filled pen has not been tested.

2.6 Dosage Modifications for Cytopenias, Abnormal Liver Enzymes, or Infections

Dosage Modifications for Patients with Rheumatoid Arthritis

- Laboratory Abnormalities: Modify dosage in case of neutropenia, thrombocytopenia, or liver enzyme elevations as shown in Table 1 [see Warnings and Precautions (5.2) and Clinical Pharmacology (12.2)]. For treatment initiation criteria, refer to the dosage recommendations for RA [see Dosage and Administration (2.1, 2.2)].

Table 1: Dosage Modifications due to Neutropenia, Thrombocytopenia, or Elevated Liver Enzymes in Patients with Rheumatoid Arthritis
Low Absolute Neutrophil Count (ANC)
Lab Value (cells/mm^3) | Recommendation
ANC greater than 1,000 | Maintain current dosage of KEVZARA.
ANC 500 to 1,000 | Hold treatment with KEVZARA until ANC greater than 1,000. KEVZARA can then be resumed at 150 mg every two weeks and increased to 200 mg every two weeks as clinically appropriate.
ANC less than 500 | Discontinue KEVZARA.
Low Platelet Count
Lab Value (cells/mm^3) | Recommendation
50,000 to 100,000 | Hold treatment with KEVZARA until platelets greater than 100,000. KEVZARA can then be resumed at 150 mg every two weeks and increased to 200 mg every two weeks as clinically appropriate.
Less than 50,000 | If confirmed by repeat testing, discontinue KEVZARA.
Liver Enzyme Abnormalities
Lab Value | Recommendation
ALT or AST greater than ULN to 3 times ULN | Consider dosage modification of concomitant DMARDs as clinically appropriate.
ALT or AST greater than 3 times ULN to 5 times ULN | Hold treatment with KEVZARA until ALT or AST less than 3 times ULN. KEVZARA can then be resumed at 150 mg every two weeks and increased to 200 mg every two weeks as clinically appropriate.
ALT or AST greater than 5 times ULN | Discontinue KEVZARA.

- Infections: If a patient with RA develops a serious infection or an opportunistic infection, hold treatment with KEVZARA until the infection is controlled [see Warnings and Precautions (5.1)].

Dosage Modifications for Patients with Polymyalgia Rheumatica

- Laboratory Abnormalities: Discontinue KEVZARA in patients with PMR who develop the following laboratory abnormalities [see Warnings and Precautions (5.2) and Clinical Pharmacology (12.2)]:
  - neutropenia (ANC below 1,000 per mm^3 at the end of the dosing interval)
  - thrombocytopenia (platelet count below 100,000 per mm^3)
  - AST or ALT elevations 3 times above the ULN
  Dosage modifications have not been studied in patients with PMR with these conditions. For treatment initiation criteria, refer to the dosage recommendations for PMR [see Dosage and Administration (2.1, 2.3)].
- Infections: If a patient with PMR develops a serious infection or an opportunistic infection, hold treatment with KEVZARA until the infection is controlled [see Warnings and Precautions (5.1)].

Dosage Modification for Patients with Polyarticular Juvenile Idiopathic Arthritis

Dose reduction of KEVZARA has not been studied in the pJIA population. Discontinue KEVZARA if ALT >5 ULN, platelet count ≤50,000 cells/mm^3, neutrophil count <500 cells/mm^3 associated with infection. Hold KEVZARA dosing for ALT >3 to ≤5 ULN, platelet count >50,000 to ≤100,000 cells/mm^3, and neutrophil count ≥500 to <1000 cells/mm^3, and until the clinical condition has been evaluated. The decision to discontinue KEVZARA should be based upon the medical assessment of the individual patient. If appropriate, the dose of concomitant methotrexate and/or other medications should be modified or discontinued.

3 DOSAGE FORMS AND STRENGTHS

Injection: 150 mg/1.14 mL and 200 mg/1.14 mL clear and colorless to pale-yellow solution in a single-dose pre-filled syringe.

Injection: 150 mg/1.14 mL and 200 mg/1.14 mL clear and colorless to pale-yellow solution in a single-dose pre-filled pen.

4 CONTRAINDICATIONS

KEVZARA is contraindicated in patients with known hypersensitivity to sarilumab or any of the inactive ingredients [see Warnings and Precautions (5.5) and Adverse Reactions (6.1)].

5 WARNINGS AND PRECAUTIONS

5.1 Serious Infections

Serious and sometimes fatal infections due to bacterial, mycobacterial, invasive fungal, viral, or other opportunistic pathogens have been reported in patients receiving immunosuppressive agents including KEVZARA. Among opportunistic infections, tuberculosis, candidiasis, and pneumocystis were reported with KEVZARA. Some patients presented with disseminated rather than localized disease and were often taking concomitant immunosuppressants such as methotrexate or corticosteroids. The most frequently observed serious infections with KEVZARA in RA patients included pneumonia and cellulitis [see Adverse Reactions (6.1)]. While not reported in KEVZARA clinical studies, other serious infections (e.g., histoplasmosis, cryptococcus, aspergillosis) have been reported in patients receiving other immunosuppressive agents for the treatment of RA.

Avoid use of KEVZARA in patients with an active infection, including localized infections. Consider the risks and benefits of treatment prior to initiating KEVZARA in patients who have:

- chronic or recurrent infection;
- a history of serious or opportunistic infections;
- underlying conditions that may predispose them to infection;
- been exposed to tuberculosis; or
- lived in or traveled to areas of endemic tuberculosis or endemic mycoses.

Closely monitor patients for the development of signs and symptoms of infection during treatment with KEVZARA, as signs and symptoms of acute inflammation may be lessened due to suppression of the acute phase reactants [see Dosage and Administration (2.6), Adverse Reactions (6.1)].

Hold treatment with KEVZARA if a patient develops a serious infection or an opportunistic infection.

Perform prompt and complete diagnostic testing appropriate for an immunocompromised patient who develops a new infection during treatment with KEVZARA; initiate appropriate antimicrobial therapy, and closely monitor the patient.

Tuberculosis

Evaluate patients for tuberculosis (TB) risk factors and test for latent infection prior to initiating treatment with KEVZARA. Treat patients with latent TB with standard antimycobacterial therapy before initiating KEVZARA. Consider anti-TB therapy prior to initiation of KEVZARA in patients with a past history of latent or active TB in whom an adequate course of treatment cannot be confirmed, and for patients with a negative test for latent TB but having risk factors for TB infection. When considering anti-TB therapy, consultation with a physician with expertise in TB may be appropriate.

Closely monitor patients for the development of signs and symptoms of TB including patients who tested negative for latent TB infection prior to initiating therapy.

Viral Reactivation

Viral reactivation has been reported with immunosuppressive biologic therapies. Cases of herpes zoster were observed in clinical studies with KEVZARA [see Adverse Reactions (6.1)]. The risk of Hepatitis B reactivation with KEVZARA is unknown since patients who were at risk for reactivation were excluded.

5.2 Laboratory Abnormalities

Neutropenia

Treatment with KEVZARA was associated with a higher incidence of decrease in absolute neutrophil count (ANC), including neutropenia [see Adverse Reactions (6.1)].

- Assess neutrophil count prior to initiation of KEVZARA and monitor neutrophil count 4 to 8 weeks after start of therapy and every 3 months thereafter [see Clinical Pharmacology (12.2)]. For recommendations regarding initiating KEVZARA therapy and dosage modifications based on ANC results see Dosage and Administration (2.1 and 2.6).
- Based on the pharmacodynamics of the changes in ANC [see Clinical Pharmacology (12.2)], use results obtained at the end of the dosing interval when considering dosage modification.

Thrombocytopenia

Treatment with KEVZARA was associated with a reduction in platelet counts in clinical studies [see Adverse Reactions (6.1)].

- Assess platelet count prior to initiation of KEVZARA and monitor platelets 4 to 8 weeks after start of therapy and every 3 months thereafter. For recommendations regarding initiating KEVZARA therapy and dosage modifications based on platelet counts see Dosage and Administration (2.1 and 2.6).

Elevated Liver Enzymes

Treatment with KEVZARA was associated with a higher incidence of transaminase elevations. These elevations were transient and did not result in any clinically evident hepatic injury in clinical studies [see Adverse Reactions (6.1)]. Increased frequency and magnitude of these elevations were observed when potentially hepatotoxic drugs (e.g., MTX) were used in combination with KEVZARA.

- Assess ALT/AST levels prior to initiation of KEVZARA and monitor ALT and AST levels 4 to 8 weeks after start of therapy and every 3 months thereafter. When clinically indicated, consider other liver function tests such as bilirubin. For recommendations regarding initiating KEVZARA therapy and dosage modifications based on transaminase elevations see Dosage and Administration (2.1 and 2.6).

Lipid Abnormalities

Treatment with KEVZARA was associated with increases in lipid parameters such as LDL cholesterol, HDL cholesterol and/or triglycerides [see Adverse Reactions (6.1)].

- Assess lipid parameters approximately 4 to 8 weeks following initiation of treatment with KEVZARA, then at approximately 6-month intervals.
- Manage patients according to clinical guidelines for the management of hyperlipidemia.

5.3 Gastrointestinal Perforation

Gastrointestinal perforations have been reported in clinical studies, primarily as complications of diverticulitis. GI perforation risk may be increased with concurrent diverticulitis or concomitant use of NSAIDs or corticosteroids. Promptly evaluate patients presenting with new onset abdominal symptoms [see Adverse Reactions (6.1)].

5.4 Immunosuppression

Treatment with immunosuppressants may result in an increased risk of malignancies. The impact of treatment with KEVZARA on the development of malignancies is not known but malignancies were reported in clinical studies [see Adverse Reactions (6.1)].

5.5 Hypersensitivity Reactions

Hypersensitivity reactions have been reported in association with KEVZARA [see Adverse Reactions (6.1)]. Hypersensitivity reactions that required treatment discontinuation were reported in 0.3% of patients in controlled RA trials. Injection site rash, rash, and urticaria were the most frequent hypersensitivity reactions. Advise patients to seek immediate medical attention if they experience any symptoms of a hypersensitivity reaction. If anaphylaxis or other hypersensitivity reaction occurs, stop administration of KEVZARA immediately. Do not administer KEVZARA to patients with known hypersensitivity to sarilumab [see Contraindications (4) and Adverse Reactions (6.1)].

5.6 Active Hepatic Disease and Hepatic Impairment

Treatment with KEVZARA is not recommended in patients with active hepatic disease or hepatic impairment, as treatment with KEVZARA was associated with transaminase elevations [see Adverse Reactions (6.1), Use in Specific Populations (8.6)].

5.7 Live Vaccines

Avoid concurrent use of live vaccines during treatment with KEVZARA due to potentially increased risk of infections; clinical safety of live vaccines during KEVZARA treatment has not been established. No data are available on the secondary transmission of infection from persons receiving live vaccines to patients receiving KEVZARA. Prior to initiating treatment, it is recommended that all patients be brought up to date with all immunizations in agreement with current immunization guidelines. The interval between live vaccinations and initiation of KEVZARA therapy should be in accordance with current vaccination guidelines regarding immunosuppressive agents [see Drug Interactions (7.3)].

6 ADVERSE REACTIONS

The following serious adverse reactions are described elsewhere in labeling:

- Serious infections [see Warnings and Precautions (5.1)]
- Neutropenia, thrombocytopenia, elevated liver enzymes, lipid abnormalities [see Warnings and Precautions (5.2)]
- Gastrointestinal perforation [see Warnings and Precautions (5.3)]
- Immunosuppression [see Warnings and Precautions (5.4)]
- Hypersensitivity reactions [see Warnings and Precautions (5.5)]

6.1 Clinical Trials Experience

Because clinical studies are conducted under widely varying conditions, adverse reaction rates observed in the clinical studies of a drug cannot be directly compared to rates in the clinical studies of another drug and may not reflect the rates observed in practice.

Rheumatoid Arthritis

All patients in the safety data described below had moderately to severely active rheumatoid arthritis.

The safety of KEVZARA in combination with conventional DMARDs was evaluated based on data from seven studies, of which two were placebo-controlled, consisting of 2887 patients (long-term safety population). Of these, 2170 patients received KEVZARA for at least 24 weeks, 1546 for at least 48 weeks, 1020 for at least 96 weeks, and 624 for at least 144 weeks.

The pre-rescue placebo-controlled population includes patients from the two Phase 3 efficacy studies (Studies 1 and 2) from weeks 0 to 16 for Study 1 and weeks 0 to 12 for Study 2, and was used to assess common adverse reactions and laboratory abnormalities prior to patients being permitted to switch from placebo to KEVZARA. In this population, 582 patients, 579 patients, and 579 patients received KEVZARA 200 mg, KEVZARA 150 mg, or placebo once every two weeks, respectively, in combination with conventional DMARDs.

The 52-week placebo-controlled population includes patients from one Phase 2 study of 12-week duration and two Phase 3 efficacy studies (one of 24-week duration and the other of 52-week duration). This placebo-controlled population includes all subjects from the double-blind, placebo-controlled periods from each study and was analyzed under their original randomization assignment. In this population, 661 patients, 660 patients, and 661 patients received KEVZARA 200 mg, KEVZARA 150 mg, or placebo once every two weeks, respectively, in combination with conventional DMARDs.

Most safety data are described for the pre-rescue population. For rarer events, the 52-week placebo-controlled population is used.

The most common serious adverse reactions were infections.

The most frequent adverse reactions (occurring in at least 3% of patients treated with KEVZARA in combination with DMARDs) observed with KEVZARA in the clinical studies were neutropenia, increased ALT, injection site erythema, upper respiratory infections, and urinary tract infections.

In the pre-rescue placebo-controlled population, premature discontinuation due to adverse reactions occurred in 8%, 6% and 3% of patients treated with KEVZARA 200 mg, KEVZARA 150 mg, and placebo, respectively.

The most common adverse reaction (greater than 1%) that resulted in discontinuation of therapy with KEVZARA was neutropenia.

The use of KEVZARA as monotherapy was assessed in 132 patients, of which 67 received KEVZARA 200 mg and 65 patients received KEVZARA 150 mg without concomitant DMARDs. The safety profile was generally consistent with that in the population receiving concomitant DMARDs.

Overall Infections

In the pre-rescue placebo-controlled population, the rate of infections in the 200 mg and 150 mg KEVZARA + DMARD group was 110 and 105 events per 100 patient-years, respectively, compared to 81 events per 100 patient-years in the placebo + DMARD group. The most commonly reported infections (2% to 4% of patients) were upper respiratory tract infections, urinary tract infections, and nasopharyngitis.

In the 52-week placebo-controlled population, 0.8% of patients (5 patients) treated with KEVZARA 200 mg + DMARD, 0.6% (4 patients) treated with KEVZARA 150 mg + DMARD and 0.5% (3 patients) treated with placebo + DMARD had an event of herpes zoster [see Warnings and Precautions (5.1)].

The overall rate of infections with KEVZARA + DMARD in the long-term safety population was consistent with rates in the controlled periods of the studies.

Serious Infections

In the pre-rescue population, the rate of serious infections in the 200 mg and 150 mg KEVZARA + DMARD group was 3.8 and 4.4 events per 100 patient-years, respectively, compared to 2.5 events per 100 patient-years in the placebo + DMARD group. In the 52-week placebo-controlled population, the rate of serious infections in the 200 mg and 150 mg KEVZARA + DMARD group was 4.3 and 3.0 events per 100 patient-years, respectively, compared to 3.1 events per 100 patient-years in the placebo + DMARD group.

In the long-term safety population, the overall rate of serious infections was consistent with rates in the controlled periods of the studies. The most frequently observed serious infections included pneumonia and cellulitis. Cases of opportunistic infection have been reported [see Warnings and Precautions (5.1)].

Gastrointestinal Perforation

In the 52-week placebo-controlled population, one patient on KEVZARA therapy experienced a gastrointestinal (GI) perforation (0.11 events per 100 patient-years).

In the long-term safety population, the overall rate of GI perforation was consistent with rates in the controlled periods of the studies. Reports of GI perforation were primarily reported as complications of diverticulitis including lower GI perforation and abscess. Most patients who developed GI perforations were taking concomitant nonsteroidal anti-inflammatory medications (NSAIDs) or corticosteroids. The contribution of these concomitant medications relative to KEVZARA in the development of GI perforations is not known [see Warnings and Precautions (5.3)].

Hypersensitivity Reactions

In the pre-rescue placebo-controlled population, the proportion of patients who discontinued treatment due to hypersensitivity reactions was higher among those treated with KEVZARA (0.3% in 200 mg, 0.2% in 150 mg) than placebo (0%). The rate of discontinuations due to hypersensitivity in the long-term safety population was consistent with the placebo-controlled period.

Injection Site Reactions

In the pre-rescue placebo-controlled population, injection site reactions were reported in 7% of patients receiving KEVZARA 200 mg, 6% receiving KEVZARA 150 mg, and 1% receiving placebo. These injection site reactions (including erythema and pruritus) were mild in severity for the majority of patients and necessitated drug discontinuation in 2 (0.2%) patients receiving KEVZARA.

Laboratory Abnormalities

Decreased neutrophil count

In the pre-rescue placebo-controlled population, decreases in neutrophil counts less than 1000 per mm^3 occurred in 6% and 4% of patients in the 200 mg KEVZARA + DMARD and 150 mg KEVZARA + DMARD group, respectively, compared to no patients in the placebo + DMARD groups. Decreases in neutrophil counts less than 500 per mm^3 occurred in 0.7% of patients in both the 200 mg KEVZARA + DMARD and 150 mg KEVZARA + DMARD groups. Decrease in ANC was not associated with the occurrence of infections, including serious infections.

In the long-term safety population, the observations on neutrophil counts were consistent with what was seen in the placebo-controlled clinical studies [see Warnings and Precautions (5.2)].

Decreased platelet count

In the pre-rescue placebo-controlled population, decreases in platelet counts less than 100,000 per mm^3 occurred in 1% and 0.7% of patients on 200 mg and 150 mg KEVZARA + DMARD, respectively, compared to no patients on placebo + DMARD, without associated bleeding events.

In the long-term safety population, the observations on platelet counts were consistent with what was seen in the placebo-controlled clinical studies [see Warnings and Precautions (5.2)].

Elevated liver enzymes

Liver enzyme elevations in the pre-rescue placebo-controlled population (KEVZARA + DMARD or placebo + DMARD) are summarized in Table 2. In patients experiencing liver enzyme elevation, modification of treatment regimen, such as interruption of KEVZARA or reduction in dose, resulted in decrease or normalization of liver enzymes [see Dosage and Administration (2.6)]. These elevations were not associated with clinically relevant increases in direct bilirubin, nor were they associated with clinical evidence of hepatitis or hepatic impairment [see Warnings and Precautions (5.2)].

Table 2: Incidence of Liver Enzyme Elevations in Adults with Moderately to Severely Active Rheumatoid Arthritis [Phase 3 placebo-controlled safety population through the pre-rescue period]
 | Placebo + DMARD N=579 | KEVZARA 150 mg + DMARD N=579 | KEVZARA 200 mg + DMARD N=582
AST
Greater than ULN to 3 times ULN or less | 15% | 27% | 30%
Greater than 3 times ULN to 5 times ULN | 0% | 1% | 1%
Greater than 5 times ULN | 0% | 0.7% | 0.2%
ALT
Greater than ULN to 3 times ULN or less | 25% | 38% | 43%
Greater than 3 times ULN to 5 times ULN | 1% | 4% | 3%
Greater than 5 times ULN | 0% | 1% | 0.7%
ULN = Upper Limit of Normal

Lipid Abnormalities

Lipid parameters (LDL, HDL, and triglycerides) were first assessed at 4 weeks following initiation of KEVZARA + DMARDs in the placebo-controlled population. Increases were observed at this time point with no additional increases observed thereafter. Changes in lipid parameters from baseline to Week 4 are summarized below:

- Mean LDL increased by 12 mg/dL in the KEVZARA 150 mg every two weeks + DMARD group and 16 mg/dL in the KEVZARA 200 mg every two weeks + DMARD group.
- Mean triglycerides increased by 20 mg/dL in the KEVZARA 150 mg every two weeks + DMARD group and 27 mg/dL in the KEVZARA 200 mg every two weeks + DMARD group.
- Mean HDL increased by 3 mg/dL in both the KEVZARA 150 mg every two weeks + DMARD and KEVZARA 200 mg every two weeks + DMARD groups.

In the long-term safety population, the observations in lipid parameters were consistent with what was observed in the placebo-controlled clinical studies.

Malignancies

In the 52-week placebo-controlled population, 9 malignancies (exposure-adjusted event rate of 1.0 event per 100 patient-years) were diagnosed in patients receiving KEVZARA + DMARD compared to 4 malignancies in patients in the control group (exposure-adjusted event rate of 1.0 event per 100 patient-years).

In the long-term safety population, the rate of malignancies was consistent with the rate observed in the placebo-controlled period [see Warnings and Precautions (5.4)].

Other Adverse Reactions

Adverse reactions occurring in 2% or more of patients on KEVZARA + DMARD and greater than those observed in patients on placebo + DMARD are summarized in Table 3.

Table 3: Common Adverse Reactions [Adverse reactions occurring in 2% or more in the 150 mg KEVZARA + DMARD or 200 mg KEVZARA + DMARD groups and greater than observed in Placebo + DMARD] in Adults with Moderately to Severely Active Rheumatoid Arthritis [Pre-rescue, placebo-controlled population]
Adverse Reactions | Placebo + DMARD (N=579) | KEVZARA 150 mg + DMARD (N=579) | KEVZARA 200 mg + DMARD (N=582)
Neutropenia | 0.2% | 7% | 10%
Alanine aminotransferase increased | 2% | 5% | 5%
Injection site erythema | 0.9% | 5% | 4%
Injection site pruritus | 0.2% | 2% | 2%
Upper respiratory tract infection | 2% | 4% | 3%
Urinary tract infection | 2% | 3% | 3%
Hypertriglyceridemia | 0.5% | 3% | 1%
Leukopenia | 0% | 0.9% | 2%

Medically relevant adverse reactions occurring at an incidence less than 2% in patients with rheumatoid arthritis treated with KEVZARA in controlled studies was oral herpes.

Polymyalgia Rheumatica

Safety has been studied in one Phase 3 study (Study 3) in 117 PMR patients of whom 59 received subcutaneous KEVZARA 200 mg [see Clinical Studies (14.2)]. Of these, 45 patients received KEVZARA for at least 24 weeks, 44 patients for at least 40 weeks, and 10 patients for at least 52 weeks. The total patient years duration in the KEVZARA PMR population was 47.37 patient years during the 12-month double blind, placebo-controlled study.

The common adverse reactions occurring in ≥5% of patients treated with KEVZARA were neutropenia (15.3%), leukopenia (6.8%), constipation (6.8%), rash pruritic (5.1%), myalgia (6.8%), fatigue (5.1%), and injection site pruritus (5.1%).

Serious adverse reactions of neutropenia occurred in 2 patients (3.4%) in the KEVZARA group compared to none in the placebo group. In both cases of neutropenia, the participants had a neutrophil count less than 500 per mm^3 without any infections and resolved following permanent discontinuation of study drug.

The most common adverse reactions that resulted in permanent discontinuation of therapy with KEVZARA were neutropenia in 3 patients (5.1%) and infection in 3 separate patients (5.1%), including COVID-19 (n=1), intervertebral discitis (n=1), and pneumonia (n=1).

Overall Infections

In Study 3, the proportion of patients with infections was lower in the KEVZARA group (37.3%) compared to the placebo group (50.0%). Two patients (3.2%) in the KEVZARA group and 1 patient (1.7%) in the placebo group had an event of herpes zoster.

Serious infections

In Study 3, the proportion of patients with serious infections was similar in the KEVZARA group (5.1%) compared to the placebo group (5.2%).

Injection Site Reactions

In Study 3, three patients (5.1%) in the KEVZARA group experienced injection site reactions of pruritus which were mild in severity. No patient in the placebo group experienced injection site reactions.

Laboratory Abnormalities

Decreased neutrophil count

In Study 3, decreases in neutrophil counts less than 1,000 per mm^3 occurred in 12% of the KEVZARA treated group and no patient in the placebo treated group. Decreases in neutrophil counts less than 500 per mm^3 occurred in 3.4% of patients in KEVZARA treated group compared to no patient in the placebo treated group.

Decreased platelet count

In Study 3, decreases in platelet counts between 75,000 to 100,000 per mm^3 occurred in two patients (3.4%) in the KEVZARA group, compared to no patient in the placebo treated group. These platelet count decreases were transient and not associated with bleeding events.

Elevated liver enzymes

In Study 3, no KEVZARA treated patients had an ALT or AST greater than 3 times the upper limit of normal (ULN). In the placebo treated group, 2 patients had ALT elevations greater than 3 times the ULN.

Lipid Abnormalities

In Study 3, cholesterol levels ≥299.27 mg/dL were observed in 8/58 (13.8%) patients in the KEVZARA group compared to 4/58 (6.9%) patients in the placebo group. Triglycerides ≥407.4 mg/dL were observed in 3/58 (5.2%) patients in the KEVZARA group compared to 1/58 (1.7%) in the placebo group.

No significant differences in mean HDL between KEVZARA group and placebo group were observed. At Week 52, mean increase from baseline for LDL and triglycerides levels were observed in the KEVZARA group though both remained within the normal range.

Polyarticular Juvenile Idiopathic Arthritis (pJIA)

The safety of KEVZARA was studied in patients 2 to 17 years of age with pJIA who have had an inadequate response to current therapy (Study 4) [see Clinical Studies (14.3)]. A total of 93 patients received at least one administration of the recommended dose: 79 (84.9%) patients received the recommended dose for 52 weeks, 53 (57%) patients received it for 96 weeks and 30 (32.2%) patients received it for 156 weeks.

The overall median duration of study treatment for the recommended dose was 672 days. The cumulative exposure to treatment for patients who received the recommended dose at any time during the study was 184.1 patient-years.

The most common adverse drug reactions were nasopharyngitis, neutropenia, upper respiratory tract infection, and injection site erythema.

The most common adverse drug reaction that resulted in permanent discontinuation of therapy with KEVZARA was neutropenia (5.4%).

No new adverse reactions and safety concerns were identified in the pJIA population compared to the RA population.

Infections

In Study 4, the rate of infections was 146.6 events per 100 patient-years. The most common infections observed were nasopharyngitis (36.6%) and upper respiratory tract infections (URTI) (14.0%).

Injection Site Reactions

In Study 4, injection site reactions (ISRs) occurred in 13 (14.0%) patients and the most commonly reported ISR was injection site erythema (9.7%). The majority of these events were mild and none of the ISRs required patient withdrawal from treatment or dose interruption.

Laboratory Abnormalities

Decrease neutrophil count

In Study 4, decreases in neutrophil counts less than 1000 per mm^3 occurred in 10/52 (19.2%) patients weighing in ≥30 kg and 20/41 (48.8%) patients weighing 10 to <30 kg. The frequency of decreased neutrophil count was higher until Week 12. Decrease in ANC was not associated with an occurrence of infections, including serious infections.

Decrease monocyte count

In Study 4, decrease in monocyte counts occurred in 4 (4.3%) patients and were mild in severity and non-serious.

Elevated liver enzymes

In Study 4, nine (9.7%) patients had ALT increases, including one (1.1%) patient who had ALT >3 times upper limit of normal (ULN) and up to ≤5 times ULN, and two (2.2%) patients who had ALT increases >5 times ULN and up to ≤10 times ULN that resulted in permanent discontinuation. All patients recovered.

Lipid Abnormalities

In Study 4, triglyceride levels of ≥150 mg/dL (1 × ULN) were observed in one (1.1%) patient. Three (3.2%) patients overall had elevation in triglycerides, and all were mild in severity and non-serious. No significant changes in mean LDL, HDL or total cholesterol were observed during the entire 156-week treatment period.

7 DRUG INTERACTIONS

7.1 Use with Other Drugs

Population pharmacokinetic analyses did not detect any effect of methotrexate (MTX) on sarilumab clearance. KEVZARA has not been investigated in combination with JAK inhibitors or biological DMARDs such as TNF antagonists [see Dosage and Administration (2.2)].

7.2 Interactions with CYP450 Substrates

Various in vitro and limited in vivo human studies have shown that cytokines and cytokine modulators can influence the expression and activity of specific cytochrome P450 (CYP) enzymes and therefore have the potential to alter the pharmacokinetics of concomitantly administered drugs that are substrates of these enzymes. Elevated interleukin-6 (IL-6) concentration may down-regulate CYP activity such as in patients with RA and hence increase drug levels compared to subjects without RA. Blockade of IL-6 signaling by IL-6Rα antagonists such as KEVZARA might reverse the inhibitory effect of IL-6 and restore CYP activity, leading to altered drug concentrations.

The modulation of IL-6 effect on CYP enzymes by KEVZARA may be clinically relevant for CYP substrates with a narrow therapeutic index, where the dose is individually adjusted. Upon initiation or discontinuation of KEVZARA, in patients being treated with CYP substrate medicinal products, perform therapeutic monitoring of effect (e.g., warfarin) or drug concentration (e.g., theophylline) and adjust the individual dose of the medicinal product as needed.

Exercise caution when co-administering KEVZARA with CYP3A4 substrate drugs where decrease in effectiveness is undesirable, e.g., oral contraceptives, lovastatin, atorvastatin, etc. The effect of KEVZARA on CYP450 enzyme activity may persist for several weeks after stopping therapy [see Clinical Pharmacology (12.3)].

7.3 Live Vaccines

Avoid concurrent use of live vaccines during treatment with KEVZARA [see Warnings and Precautions (5.7)].

8 USE IN SPECIFIC POPULATIONS

8.1 Pregnancy

Risk Summary

The limited human data with KEVZARA in pregnant women are not sufficient to inform drug-associated risk for major birth defects and miscarriage. Monoclonal antibodies, such as sarilumab, are actively transported across the placenta during the third trimester of pregnancy and may affect immune response in the in utero exposed infant (see Clinical Considerations). From animal data, and consistent with the mechanism of action, levels of IgG, in response to antigen challenge, may be reduced in the fetus/infant of treated mothers (see Clinical Considerations and Data). In an animal reproduction study, consisting of a combined embryo-fetal and pre- and postnatal development study with monkeys that received intravenous administration of sarilumab, there was no evidence of embryotoxicity or fetal malformations with exposures up to approximately 84 times the maximum recommended human dose (MRHD) (see Data). The literature suggests that inhibition of IL-6 signaling may interfere with cervical ripening and dilatation and myometrial contractile activity leading to potential delays of parturition (see Data).

The estimated background risk of major birth defects and miscarriage for the indicated population is unknown. All pregnancies have a background risk of birth defect, loss, or other adverse outcomes. In the U.S. general population, the estimated background risk of major birth defects and miscarriages in clinically recognized pregnancies is 2% to 4% and 15% to 20%, respectively. KEVZARA should be used in pregnancy only if the potential benefit justifies the potential risk to the fetus.

Clinical Considerations

Fetal/Neonatal Adverse Reactions

Monoclonal antibodies are increasingly transported across the placenta as pregnancy progresses, with the largest amount transferred during the third trimester. Risks and benefits should be considered prior to administering live or live-attenuated vaccines to infants exposed to KEVZARA in utero [see Warnings and Precautions (5.7)]. From the animal data, and consistent with the mechanism of action, levels of IgG, in response to antigen challenge, may be reduced in the fetus/infant of treated mothers (see Data).

Data

Animal Data

In a combined embryo-fetal and pre- and postnatal development study, pregnant cynomolgus monkeys received sarilumab at intravenous doses of 0, 5, 15, or 50 mg/kg/week from confirmation of pregnancy at gestation day (GD) 20, throughout the period of organogenesis (up to approximately GD 50), and continuing to natural birth of infants at around GD 165. Maintenance of pregnancy was not affected at any doses. Sarilumab was not embryotoxic or teratogenic with exposures up to approximately 84 times the MRHD (based on AUC with maternal intravenous doses up to 50 mg/kg/week). Sarilumab had no effect on neonatal growth and development evaluated up to one month after birth. Sarilumab was detected in the serum of neonates up to one month after birth, suggesting that the antibody had crossed the placenta.

Following antigen challenge, decreased IgG titers attributed to the immunosuppressive action of sarilumab were evident in studies with older monkeys, with exposures up to approximately 80 times the MRHD (based on AUC with intravenous doses up to 50 mg/kg/week) and juvenile mice treated with an analogous antibody, which binds to murine IL-6Rα to inhibit IL-6 mediated signaling, at subcutaneous doses up to 200 mg/kg/week. These findings suggest the potential for decreased IgG titers, following antigen challenge, in infants of mothers treated with KEVZARA.

Parturition is associated with significant increases of IL-6 in the cervix and myometrium. The literature suggests that inhibition of IL-6 signaling may interfere with cervical ripening and dilatation and myometrial contractile activity leading to potential delays of parturition. For mice deficient in IL-6 (ll6-/- null mice), parturition was delayed relative to wild-type (ll6+/+) mice. Administration of recombinant IL-6 to ll6-/- null mice restored the normal timing of delivery.

8.2 Lactation

Risk Summary

No information is available on the presence of sarilumab in human milk, the effects of the drug on the breastfed infant, or the effects of the drug on milk production. Maternal IgG is present in human milk. If sarilumab is transferred into human milk, the effects of local exposure in the gastrointestinal tract and potential limited systemic exposure in the infant to sarilumab are unknown. The lack of clinical data during lactation precludes clear determination of the risk of KEVZARA to an infant during lactation; therefore, the developmental and health benefits of breastfeeding should be considered along with the mother's clinical need for KEVZARA and the potential adverse effects on the breastfed child from KEVZARA or from the underlying maternal condition.

8.4 Pediatric Use

KEVZARA is approved for active polyarticular juvenile idiopathic arthritis (pJIA) in pediatric patients who weigh 63 kg or greater. Use of KEVZARA in this patient population is supported by evidence from adequate and well-controlled studies of KEVZARA in adults with RA, pharmacokinetic data from adult patients with RA, and a pharmacokinetic, pharmacodynamic, dose-finding, and safety study in pediatric patients with pJIA 2 years of age and older. KEVZARA is not approved in pediatric patients weighing less than 63 kg because of the lack of an appropriate dosage form [see Adverse Reactions (6.1), Pharmacokinetics (12.3), and Clinical Studies (14.1, 14.3)].

The safety and effectiveness of KEVZARA have not been established in pediatric patients with pJIA below the age of 2 years.

8.5 Geriatric Use

Of the total number of patients with RA exposed to KEVZARA in clinical studies [see Clinical Studies (14.1)], 450 patients (15%) were 65 years of age and over, while 48 patients (1.6%) were 75 years and over. In clinical studies, no overall differences in safety and efficacy were observed between older and younger patients. The frequency of serious infections among KEVZARA and placebo-treated patients 65 years of age and older was higher than those under the age of 65.

Of the total number of patients with PMR exposed to KEVZARA in the clinical study (Study 3) [see Clinical Studies (14.2)], 16 patients (27.1%) were under 65 years of age, 33 patients (55.9%) were 65 to 75 years of age, and 10 patients (17.0%) were 75 years and over. The median age in the PMR study was 69.0 years and all patients were on baseline corticosteroid. There were no differences in the incidence of serious infections between the KEVZARA group and placebo group. In Study 3, no overall differences in safety were observed between older and younger patients.

As there is a higher incidence of infections in the elderly population in general, caution should be used when treating the elderly.

8.6 Hepatic Impairment

The safety and efficacy of KEVZARA have not been studied in patients with hepatic impairment, including patients with positive HBV or HCV serology [see Warnings and Precautions (5.6)].

8.7 Renal Impairment

No dose adjustment is required in patients with mild to moderate renal impairment. KEVZARA has not been studied in patients with severe renal impairment [see Clinical Pharmacology (12.3)].

11 DESCRIPTION

Sarilumab is a human recombinant monoclonal antibody of the IgG1 subclass that binds to the IL-6 receptor and has an approximate molecular weight of 150 kDa. Sarilumab is produced by recombinant DNA technology in Chinese Hamster Ovary cell suspension culture.

KEVZARA (sarilumab) injection for subcutaneous administration is supplied as a sterile, clear and colorless to pale yellow, preservative-free solution of approximately pH 6.0. KEVZARA is supplied in a single-dose pre-filled syringe and pre-filled pen.

Each syringe or pen delivers 1.14 mL of solution containing 150 mg or 200 mg of sarilumab, arginine (8.94 mg), histidine (3.71 mg), polysorbate 20 (2.28 mg), sucrose (57 mg) and Water for Injection, USP.

12 CLINICAL PHARMACOLOGY

12.1 Mechanism of Action

Sarilumab binds to both soluble and membrane-bound IL-6 receptors (sIL-6R and mIL-6R), and has been shown to inhibit IL-6-mediated signaling through these receptors. IL-6 is a pleiotropic pro-inflammatory cytokine produced by a variety of cell types including T- and B-cells, lymphocytes, monocytes, and fibroblasts. IL-6 has been shown to be involved in diverse physiological processes such as T-cell activation, induction of immunoglobulin secretion, initiation of hepatic acute phase protein synthesis, and stimulation of hematopoietic precursor cell proliferation and differentiation. IL-6 is also produced by synovial and endothelial cells leading to local production of IL-6 in joints affected by inflammatory processes such as rheumatoid arthritis.

12.2 Pharmacodynamics

Following single-dose subcutaneous administration of sarilumab 200-mg and 150-mg in patients with RA, rapid reduction of CRP levels was observed. Levels were reduced to normal within 2 weeks after treatment initiation. Following single-dose sarilumab administration, in patients with RA, absolute neutrophil counts decreased to the nadir between 3 to 4 days and thereafter recovered towards baseline [see Warnings and Precautions (5.2)]. Treatment with sarilumab resulted in decreases in fibrinogen and serum amyloid A, and increases in hemoglobin and serum albumin. In patients with pJIA, decreases in CRP, erythrocyte sedimentation rate (ESR) and neutrophil count were observed after KEVZARA administration.

12.3 Pharmacokinetics

Rheumatoid Arthritis

Absorption

The pharmacokinetics of sarilumab were characterized in 1770 adult patients with rheumatoid arthritis (RA) treated with sarilumab which included 631 patients treated with 150 mg and 682 patients treated with 200 mg doses by subcutaneous injection every two weeks for up to 52 weeks. The median tmax was observed in 2 to 4 days.

At steady state, exposure over the dosing interval measured by area under curve (AUC) increased 2-fold with an increase in dose from 150 to 200 mg every two weeks. Steady state was reached in 14 to 16 weeks with a 2- to 3-fold accumulation compared to single dose exposure.

For the 150 mg every two weeks dose regimen, the estimated mean (± SD) steady-state AUC, Cmin and Cmax of sarilumab were 202 ± 120 mg.day/L, 6.35 ± 7.54 mg/L, and 20.0 ± 9.20 mg/L, respectively.

For the 200 mg every two weeks dose regimen, the estimated mean (± SD) steady-state AUC, Cmin and Cmax of sarilumab were 395 ± 207 mg.day/L, 16.5 ± 14.1 mg/L, and 35.6 ± 15.2 mg/L, respectively.

Distribution

In patients with RA, the apparent volume of distribution at steady state was 7.3 L.

Elimination

Sarilumab is eliminated by parallel linear and non-linear pathways. At higher concentrations, the elimination is predominantly through the linear, non-saturable proteolytic pathway, while at lower concentrations, non-linear saturable target-mediated elimination predominates. The half-life of sarilumab is concentration-dependent. At 200 mg every 2 weeks, the concentration-dependent half-life is up to 10 days in patients with RA at steady state. At 150 mg every 2 weeks, the concentration-dependent half-life is up to 8 days in patients with RA at steady state.

After the last steady state dose of 150 mg and 200 mg sarilumab, the median times to non-detectable concentration are 28 and 43 days, respectively.

Population pharmacokinetic analyses in patients with RA revealed that there was a trend toward higher apparent clearance of sarilumab in the presence of anti-sarilumab antibodies.

Metabolism

The metabolic pathway of sarilumab has not been characterized. As a monoclonal antibody sarilumab is expected to be degraded into small peptides and amino acids via catabolic pathways in the same manner as endogenous IgG.

Excretion

Monoclonal antibodies, including sarilumab, are not eliminated via renal or hepatic pathways.

Polymyalgia Rheumatica

The pharmacokinetic profile of subcutaneous sarilumab in PMR patients was determined using a population pharmacokinetic analysis on a data set including 58 PMR patients treated with repeated subcutaneous administration of sarilumab 200 mg every two weeks. In general, pharmacokinetic exposures were higher in patients with PMR when compared to patients with RA. For this dose regimen, the estimated mean (± SD) steady-state AUC, Cmin and Cmax of sarilumab were 551 ± 321 mg.day/L, 27.0 ± 21.5 mg/L, and 46.5 ± 23.0 mg/L, respectively. The median time to steady state in PMR patients was estimated to be 28 weeks. There was accumulation following subcutaneous administration of sarilumab 200 mg, with an accumulation ratio of approximately 6-fold based on the mean trough concentrations.

Polyarticular juvenile idiopathic arthritis (pJIA)

The pharmacokinetics of sarilumab in pJIA patients was characterized by a population pharmacokinetic analysis which included 101 pediatric patients 2 to 17 years of age who were treated with repeated subcutaneous doses of sarilumab.

For 3 mg/kg sarilumab (patients with a body weight ≥30 kg) given every 2 weeks, the estimated mean (±SD) steady-state AUC, Cmin, and Cmax of sarilumab were 276 ± 121 mg.day/L, 9.57 ± 5.84 mg/L, and 27.1 ± 11.6 mg/L, respectively.

For 4 mg/kg sarilumab (patients with a body weight 10 to <30 kg) given every 2 weeks, the estimated mean (± SD) steady-state AUC, Cmin, and Cmax of sarilumab were 395 ± 101 mg.day/L, 14.4 ± 9.81 mg/L, and 40.4 ± 7.77 mg/L, respectively.

Steady state was reached in 12 to 28 weeks with a 2- to 4-fold accumulation compared to single dose exposure for 3 and 4 mg/kg q2w. Steady state concentrations were within the range of exposures in adult RA patients following 150 mg/200 mg every 2 weeks.

Specific Populations

Population pharmacokinetic analyses in adult patients showed that age, gender and race did not meaningfully influence the pharmacokinetics of sarilumab. Although body weight influenced the pharmacokinetics of sarilumab, no dose adjustments are recommended for any of these demographics in adult patients.

Hepatic Impairment

No formal study of the effect of hepatic impairment on the pharmacokinetics of sarilumab was conducted.

Renal Impairment

No formal study of the effect of renal impairment on the pharmacokinetics of sarilumab was conducted. Based on population pharmacokinetic analysis of data from 1770 patients with RA, including patients with mild (creatinine clearance (CLcr): 60 to 90 mL/min; N=471 at baseline) or moderate (CLcr: 30 to 60 mL/min; N=74 at baseline) renal impairment, CLcr was correlated with sarilumab exposure. However, the effect of CLcr on exposure is not sufficient to warrant a dose adjustment [see Use in Specific Populations (8.7)]. Patients with severe renal impairment were not studied.

Drug-Drug Interactions

CYP450 Substrates

Simvastatin is a CYP3A4 and OATP1B1 substrate. In 17 patients with RA, one week following a single 200-mg subcutaneous administration of sarilumab, exposure of simvastatin and simvastatin acid decreased by 45% and 36%, respectively [see Drug Interactions (7.2)].

12.6 Immunogenicity

As with all therapeutic proteins, there is potential for immunogenicity. The detection of antibody formation is highly dependent on the sensitivity and specificity of the assay. Additionally, the observed incidence of antibody (including neutralizing antibody) positivity in an assay may be influenced by several factors, including assay methodology, sample handling, timing of sample collection, concomitant medications, and underlying disease. For these reasons, comparison of the incidence of antibodies to sarilumab in the studies described below with the incidence of antibodies in other studies or to other products may be misleading.

In the RA pre-rescue population, 4.0% of patients treated with KEVZARA 200 mg + DMARD, 5.7% of patients treated with KEVZARA 150 mg + DMARD and 1.9% of patients treated with placebo + DMARD, exhibited an anti-drug antibody (ADA) response. Neutralizing antibodies (NAb) were detected in 1.0% of patients on KEVZARA 200 mg + DMARD, 1.6% of patients on KEVZARA 150 mg + DMARD, and 0.2% of patients on placebo + DMARD.

In RA patients treated with KEVZARA monotherapy, 9.2% of patients exhibited an ADA response with 6.9% of patients also exhibiting NAbs. Prior to administration of KEVZARA, 2.3% of patients exhibited an ADA response.

No correlation was observed between ADA development and either loss of efficacy or adverse reactions in RA patients.

In the PMR population, 1 patient (1.8%) in the KEVZARA 200 mg + 14-week corticosteroid taper group exhibited an ADA response. None of the patients in the placebo + 52-week corticosteroid taper group exhibited an ADA response. Neutralizing antibodies were detected in the PMR patient with ADA response on KEVZARA 200 mg; the patient did not demonstrate a clinical response. Because of the low occurrence of anti-drug antibodies, the effect of these antibodies on the safety, and/or effectiveness of sarilumab is unknown.

In the pJIA population, 3 (4.3%) patients treated with the recommended dose exhibited an anti-drug antibody (ADA) response. Neutralizing antibodies were detected in one pJIA patient with ADA response. Because of the low occurrence of anti-drug antibodies, the effect of these antibodies on the safety, and/or effectiveness of sarilumab is unknown.

13 NONCLINICAL TOXICOLOGY

13.1 Carcinogenesis, Mutagenesis, Impairment of Fertility

No long-term animal studies have been performed to establish the carcinogenicity potential of sarilumab. Literature indicates that the IL-6 pathway can mediate anti-tumor responses by promoting increased immune cell surveillance of the tumor microenvironment. However, available published evidence also supports that IL-6 signaling through the IL-6 receptor may be involved in pathways that lead to tumorigenesis. The malignancy risk in humans from an antibody that disrupts signaling through the IL-6 receptor, such as sarilumab, is presently unknown.

Fertility and reproductive performance were unaffected in male and female mice treated with an analogous antibody, which binds to murine IL-6Rα to inhibit IL-6 mediated signaling, at subcutaneous doses of 10, 25, and 100 mg/kg twice per week.

14 CLINICAL STUDIES

14.1 Rheumatoid Arthritis

Design of Clinical Studies in Adults with Moderately to Severely Active RA

The efficacy and safety of KEVZARA in RA were assessed in two randomized, double-blind, placebo-controlled multicenter studies (Study 1 and Study 2) in patients older than 18 years with moderately to severely active rheumatoid arthritis (RA) diagnosed according to American College of Rheumatology (ACR) criteria. Patients had at least 8 tender and 6 swollen joints at baseline.

Study 1 (NCT01061736) evaluated 1197 patients with moderately to severely active rheumatoid arthritis who had inadequate clinical response to methotrexate (MTX). Patients received subcutaneous KEVZARA 200 mg, KEVZARA 150 mg, or placebo every two weeks with concomitant MTX. After Week 16 in Study 1, patients with an inadequate response could have been rescued with KEVZARA 200 mg every two weeks.

Study 2 (NCT01146652) evaluated 546 patients with moderately to severely active rheumatoid arthritis who had an inadequate clinical response or were intolerant to one or more TNF-α antagonists. Patients received subcutaneous KEVZARA 200 mg, KEVZARA 150 mg, or placebo every two weeks with concomitant conventional DMARDs (MTX, sulfasalazine, leflunomide, and/or hydroxychloroquine). After Week 12 in Study 2, patients with an inadequate response could have been rescued with KEVZARA 200 mg every two weeks.

In Studies 1 and 2, the primary endpoint was the proportion of patients who achieved an ACR20 response at Week 24. Other key endpoints evaluated included change from baseline in HAQ-DI at Week 16 in Study 1 and at Week 12 in Study 2, and change from baseline in van der Heijde-modified Total Sharp Score (mTSS) at Week 52 in Study 1.

Clinical Response

The percentages of KEVZARA every two weeks + MTX/DMARD-treated patients achieving ACR20, ACR50 and ACR70 responses in Studies 1 and 2 are shown Table 4. In both studies, patients treated with either 200 mg or 150 mg of KEVZARA every two weeks + MTX/DMARD had higher ACR20, ACR50, and ACR70 response rates versus placebo + MTX/DMARD-treated patients at Week 24.

In Studies 1 and 2, a greater proportion of patients treated with KEVZARA 200 mg or 150 mg every two weeks plus MTX/DMARD achieved a low level of disease activity as measured by a Disease Activity Score 28-C-Reactive Protein (DAS28-CRP) <2.6 compared with placebo + MTX/DMARD at the end of the studies (Table 4). In Study 1, the proportion of patients achieving DAS28-CRP <2.6 who had at least 3 or more active joints at the end of Week 24 was 33.1%, 37.8% and 20%, in the KEVZARA 200 mg + MTX/DMARD arm, KEVZARA 150 mg + MTX/DMARD arm, and placebo arm respectively.

Table 4: Clinical Response in Placebo-Controlled Studies 1 and 2 in Adults with Moderately to Severely Active RA [Patients who were rescued or discontinued were considered non-responders for the analyses included in this table. In Study 1, at week 52, 196, 270, and 270 patients remained on placebo, KEVZARA 150 mg, and KEVZARA 200 mg respectively.]
Percentage of Patients
 | Study 1 |  |  | Study 2
 | Placebo + MTX N=398 | KEVZARA 150 mg + MTX N=400 | KEVZARA 200 mg + MTX N=399 | Placebo + DMARD(s) [DMARDs in Study 2 included MTX, sulfasalazine, leflunomide, and/or hydroxychloroquine.] N=181 | KEVZARA 150 mg + DMARD(s) N=181 | KEVZARA 200 mg + DMARD(s) N=184
ACR20
Week 12 | 34.7% | 54.0% | 64.9% | 37.6% | 54.1% | 62.5%
Difference from placebo (95% CI) [Weighted estimate of the rate difference; CI=confidence interval] |  | 19.4% (12.6%, 26.1%) | 30.2% (23.6%, 36.8%) |  | 16.6% (6.7%, 26.5%) | 25.3% (15.7%, 34.8%)
Week 24 [Primary end point] | 33.4% | 58.0% | 66.4% | 33.7% | 55.8% | 60.9%
Difference from placebo (95% CI) |  | 24.6% (18.0%, 31.3%) | 33.0% (26.5%, 39.5%) |  | 22.1% (12.6%, 31.6%) | 27.4% (17.7%, 37.0%)
Week 52 | 31.7% | 53.5% | 58.6%
Difference from placebo (95% CI) |  | 21.9% (15.2%, 28.5%) | 27.0% (20.5%, 33.6%) | NA [NA=Not Applicable as Study 2 was a 24-week study.] | NA | NA
ACR50
Week 12 | 12.3% | 26.5% | 36.3% | 13.3% | 30.4% | 33.2%
Difference from placebo (95% CI) |  | 14.2% (8.9%, 19.6%) | 24.1% (18.4%, 29.8%) |  | 17.1% (9.2%, 25.1%) | 20.1% (12.0%, 28.3%)
Week 24 | 16.6% | 37.0% | 45.6% | 18.2% | 37.0% | 40.8%
Difference from placebo (95% CI) |  | 20.4% (14.5%, 26.3%) | 29.1% (23.0%, 35.1%) |  | 18.8% (10.2%, 27.4%) | 22.8% (14.0%, 31.6%)
Week 52 | 18.1% | 40.0% | 42.9%
Difference from placebo (95% CI) |  | 21.9% (15.8%, 28.0%) | 24.8% (18.7%, 30.9%) | NA | NA | NA
ACR70
Week 12 | 4.0% | 11.0% | 17.5% | 2.2% | 13.8% | 14.7%
Difference from placebo (95% CI) |  | 7.0% (3.4%, 10.6%) | 13.5% (9.4%, 17.7%) |  | 11.6% (6.2%, 17.0%) | 12.5% (7.1%, 17.9%)
Week 24 | 7.3% | 19.8% | 24.8% | 7.2% | 19.9% | 16.3%
Difference from placebo (95% CI) |  | 12.5% (7.8%, 17.1%) | 17.5% (12.6%, 22.5%) |  | 12.7% (6.1%, 19.3%) | 9.2% (2.8%, 15.7%)
Week 52 | 9.0% | 24.8% | 26.8%
Difference from placebo (95% CI) |  | 15.7% (10.6%, 20.8%) | 17.8% (12.6%, 23.0%) | NA | NA | NA
Major clinical response [Major clinical response = ACR70 for at least 24 consecutive weeks during the 52-week period.]
Responders | 3.0% | 12.8% | 14.8% | NA | NA | NA
Difference from placebo (95% CI) |  | 9.7% (6.1%, 13.4%) | 11.8% (7.9%, 15.6%)
DAS28-CRP < 2.6 [Patients with DAS28-CRP <2.6 may have active joints.]
Week 12
Percentage of patients | 4.8% | 18.0% | 23.1% | 3.9% | 17.1% | 17.9%
Difference from placebo (95% CI) |  | 13.3% (9.0%, 17.5%) | 18.3% (13.7%, 23.0%) |  | 13.3% (7.3%, 19.3%) | 14.1% (8.0%, 20.3%)
Week 24
Percentage of patients | 10.1% | 27.8% | 34.1% | 7.2% | 24.9% | 28.8%
Difference from placebo (95% CI) |  | 17.7% (12.5%, 23.0%) | 24.0% (18.5%, 29.5%) |  | 17.7% (10.5%, 24.9%) | 21.7% (14.3%, 29.1%)

The percent ACR20 response by visit in Study 1 is shown in Figure 1. A similar response curve was observed in Study 2.

Figure 1: Percent of ACR20 Response by Visit for Study 1 (Adults with Moderately to Severely Active RA)

The results of the components of the ACR response criteria at Week 12 for Studies 1 and 2 are shown in Table 5.

Table 5: Mean Change from Baseline in Components of ACR Score at Week 12 (Prior to Rescue) in Adults with Moderately to Severely Active RA
 | Study 1 |  |  | Study 2
Component means (range/units) | Placebo + MTX (N=398) | KEVZARA 150 mg + MTX (N=400) | KEVZARA 200 mg + MTX (N=399) | Placebo + DMARD(s) (N=181) | KEVZARA 150 mg + DMARD(s) (N=181) | KEVZARA 200 mg + DMARD(s) (N=184)
Tender Joints (0–68)
Baseline | 26.80 | 27.21 | 26.50 | 29.42 | 27.66 | 29.55
Week 12 | 16.25 | 12.88 | 11.78 | 19.18 | 13.38 | 13.10
Change from baseline | -10.51 | -14.42 | -14.94 | -9.79 | -14.11 | -15.92
Swollen Joints (0–66)
Baseline | 16.68 | 16.60 | 16.77 | 20.21 | 19.60 | 19.97
Week 12 | 9.66 | 7.50 | 6.79 | 12.50 | 8.82 | 8.28
Change from baseline | -7.02 | -9.03 | -10.12 | -7.25 | -10.77 | -10.89
Pain VAS [VAS=visual analog scale] (0–100 mm)
Baseline | 63.71 | 65.48 | 66.71 | 71.57 | 71.02 | 74.86
Week 12 | 49.25 | 41.47 | 36.93 | 54.77 | 43.45 | 41.66
Change from baseline | -14.45 | -23.73 | -29.77 | -16.12 | -27.95 | -32.77
Physician global VAS (0–100 mm)
Baseline | 62.86 | 63.43 | 63.59 | 68.39 | 68.10 | 67.76
Week 12 | 39.25 | 31.32 | 28.47 | 43.73 | 33.65 | 30.18
Change from baseline | -23.63 | -31.85 | -34.84 | -24.60 | -34.92 | -36.92
Patient global VAS (0–100 mm)
Baseline | 63.70 | 64.43 | 66.49 | 68.77 | 67.71 | 70.89
Week 12 | 49.37 | 41.52 | 38.05 | 53.67 | 41.99 | 41.74
Change from baseline | -13.92 | -22.88 | -28.39 | -15.05 | -26.05 | -28.83
HAQ-DI (0–3)
Baseline | 1.61 | 1.63 | 1.69 | 1.80 | 1.72 | 1.82
Week 12 | 1.34 | 1.15 | 1.13 | 1.49 | 1.23 | 1.33
Change from baseline | -0.27 | -0.47 | -0.57 | -0.29 | -0.50 | -0.49
CRP (mg/L)
Baseline | 20.46 | 22.57 | 22.23 | 26.02 | 23.60 | 30.77
Week 12 | 19.61 | 9.24 | 3.30 | 21.72 | 9.21 | 4.58
Change from baseline | -0.58 | -13.59 | -18.31 | -3.39 | -14.24 | -25.91

Radiographic Response

In Study 1, structural joint damage was assessed radiographically and expressed as the van der Heijde-modified Total Sharp Score (mTSS) and its components, the erosion score and joint space narrowing score. Radiographs of hands and feet were obtained at baseline, 24 weeks, and 52 weeks and scored independently by at least two well-trained readers who were blinded to treatment group and visit number.

Both doses of KEVZARA + MTX were superior to placebo + MTX in the change from baseline in mTSS over 52 weeks (see Table 6). Less progression of both erosion and joint space narrowing scores over 52 weeks was reported in the KEVZARA + MTX treatment groups compared to the placebo + MTX group.

Treatment with KEVZARA + MTX was associated with significantly less radiographic progression of structural damage as compared with placebo + MTX. At Week 52, 55.6% of patients receiving KEVZARA 200 mg + MTX and 47.8% of patients receiving KEVZARA 150 mg + MTX had no progression of structural damage (as defined by a change in the Total Sharp Score of zero or less) compared with 38.7% of patients receiving placebo.

Table 6: Mean Radiographic Change from Baseline at Week 52 in Study 1 in Adults with Moderately to Severely Active RA [Week 52 analysis employs linear extrapolation method to impute missing or post-rescue data]
 | Study 1
 | Placebo + MTX (N=398) | KEVZARA 150 mg + MTX (N=400) | KEVZARA 200 mg + MTX (N=399)
Modified Total Sharp Score (mTSS)
Mean change | 2.78 | 0.90 | 0.25
LS [LS=least squares] mean difference (95% CI [CI=confidence interval]) |  | -1.88 (-2.74, -1.01) | -2.52 (-3.38, -1.66)
Erosion score
Mean change | 1.46 | 0.42 | 0.05
LS mean difference (95% CI) |  | -1.03 (-1.53, -0.53) | -1.40 (-1.90, -0.90)
Joint space narrowing score
Mean change | 1.32 | 0.47 | 0.20
LS mean difference (95% CI) |  | -0.85 (-1.34, -0.35) | -1.12 (-1.61, -0.63)

Physical Function Response

In Studies 1 and 2, physical function and disability were assessed by the Health Assessment Questionnaire Disability Index (HAQ-DI). Patients receiving KEVZARA 200 mg every two weeks + MTX/DMARD and KEVZARA 150 mg every two weeks + MTX/DMARD demonstrated greater improvement from baseline in physical function compared to placebo + MTX/DMARD at Week 16 and Week 12 in Studies 1 and 2, respectively (Table 7).

Table 7: Physical Function in Studies 1 and 2 in Adults with Moderately to Severely Active RA
 | Study 1 |  |  | Study 2
 | Week 16 |  |  | Week 12
 | Placebo + MTX (N=398) | KEVZARA 150 mg + MTX (N=400) | KEVZARA 200 mg + MTX (N=399) | Placebo + DMARD(s) (N=181) | KEVZARA 150 mg + DMARD(s) (N=181) | KEVZARA 200 mg + DMARD(s) (N=184)
HAQ-DI
Change from baseline | -0.30 | -0.54 | -0.58 | -0.29 | -0.50 | -0.49
Difference from placebo (95% CI) [Difference in adjusted mean change from baseline compared with placebo + DMARD at Week 16 (Study 1) or Week 12 (Study 2) and 95% confidence interval for that difference.] |  | -0.24 (-0.31, -0.16) | -0.26 (-0.34, -0.18) |  | -0.20 (-0.32, -0.09) | -0.21 (-0.33, -0.10)
% of patients with clinically meaningful improvement [Change from baseline greater than 0.3 units] | 42.5% | 53.8% | 57.4% | 35.9% | 47% | 51.1%

Other Health Related Outcomes

General health status was assessed by the Short Form health survey (SF-36) in Studies 1 and 2. Patients receiving KEVZARA 200 mg every two weeks + MTX/DMARD demonstrated greater improvement from baseline compared to placebo + MTX/DMARD in the physical component summary (PCS) at Week 24, but there was no evidence of a difference between the treatment groups in the mental component summary (MCS) at Week 24. Patients receiving KEVZARA 200 mg + MTX/DMARD reported greater improvement relative to placebo in the domains of Physical Functioning, Role Physical, Bodily Pain, General Health Perception, Vitality, Social Functioning and Mental Health, but not in the Role Emotional domain.

14.2 Polymyalgia Rheumatica

The efficacy and safety of KEVZARA in PMR were assessed in a randomized, double-blind, placebo-controlled, 52-week, multicenter study (Study 3) (NCT03600818) in adults with PMR diagnosed according to American College of Rheumatology/European Union League against Rheumatism (ACR/EULAR) classification criteria. Patients had at least one episode of unequivocal PMR flare while attempting to taper corticosteroids.

In Study 3, patients with active PMR were randomized to receive KEVZARA 200 mg every two weeks with a pre-defined 14-week taper of prednisone (n= 60) or placebo every two weeks with a pre-defined 52-week taper of prednisone (n=58). One participant was randomized but not treated in the KEVZARA 200 mg arm. Patients experiencing a disease flare or unable to adhere to the assigned prednisone tapering schedule could receive corticosteroids as rescue therapy.

The primary endpoint was the proportion of patients with sustained remission at Week 52. Sustained remission was defined as achievement of disease remission no later than Week 12, absence of disease flare from Week 12 through Week 52, sustained reduction of CRP (to <10 mg/L) from Week 12 through Week 52, and successful adherence to prednisone taper from Week 12 through Week 52. An additional endpoint was total cumulative corticosteroid dose over 52 weeks.

Clinical Response

The proportion of participants achieving sustained remission at Week 52 was higher in the KEVZARA arm compared to the placebo arm; this difference was statistically significant. At 52 weeks, a higher proportion of patients in the KEVZARA arm achieved each component of the sustained remission endpoint compared to the placebo. An analysis was conducted that removed all acute phase reactants (CRP and ESR) criteria from the definition of the sustained remission, given sarilumab's direct impact on acute phase reactants. The results of this analysis were consistent with the primary analysis (see Table 8).

Table 8 Clinical Response in Placebo-Controlled Study 3 in Adults with Active PMR
 |  | Placebo (N=58) | KEVZARA (N=60)
Sustained remission at Week 52
 | Number of patients with sustained remission, n (%) | 6 (10.3) | 17 (28.3)
 | Proportion difference (95% CI) vs. placebo |  | 18.0 (4.2, 31.8; p=0.0193)
Components of sustained remission at Week 52
 | Absence of signs and symptoms and CRP < 10 mg/L (disease remission [Disease remission is defined as the resolution of signs and symptoms of PMR, and normalization of CRP (<10 mg/L).]) no later than Week 12, n (%) | 22 (37.9) | 28 (46.7)
 | Absence of disease flare [Flare is defined as recurrence of signs and symptoms attributable to active PMR requiring an increase in corticosteroid dose, or elevation of ESR attributable to active PMR plus an increase in corticosteroid dose.] from Week 12 through Week 52, n (%) | 19 (32.8) | 33 (55.0)
 | Sustained reduction of CRP (<10 mg/L) from Week 12 through Week 52, n (%) | 26 (44.8) | 40 (66.7)
 | Successful adherence to prednisone taper from Week 12 through Week 52, n (%) | 14 (24.1) | 30 (50.0)
Sensitivity analysis removing acute phase reactants (CRP and ESR) from sustained remission at Week 52
 | Number of patients with sustained remission, n (%) | 8 (13.8) | 19 (31.7)
 | Proportion difference (95% CI) for sarilumab vs. placebo |  | 17.9 (3.1, 32.6)

Effect on Concomitant Corticosteroid Use

The total actual cumulative corticosteroid dose included all corticosteroids taken during the study (i.e., prednisone taper regimen per protocol, add-on prednisone prior to Week 12, corticosteroid use due to rescue, or corticosteroid use during the treatment period to manage an adverse reaction not related to PMR). The total actual cumulative prednisone equivalent corticosteroid dose was lower in the KEVZARA arm (mean [SD] 1039.5 [612.2] mg and median 777 mg) relative to the placebo arm (mean [SD] 2235.8 [839.4] mg and median 2044 mg).

14.3 Polyarticular Juvenile Idiopathic Arthritis (pJIA)

Supportive efficacy and safety data were provided from Study 4, which was a multicenter, open-label, two-phase study in patients aged 2 to 17 years of age with polyarticular juvenile idiopathic arthritis (pJIA) diagnosed according to American College Rheumatology (ACR) classification criteria who had an inadequate response to current therapy. This study was divided into a dose range finding portion and a confirmatory portion. Three doses were investigated in the 12-week core treatment phase of the dose range finding portion. Following the dose selection, patients were enrolled to receive the recommended dose [3 mg/kg every 2 weeks (q2w) in 42 patients weighing ≥30 kg (Group A) and 4 mg/kg q2w in 31 patients weighing ≥10 kg and <30 kg (Group B)]. A total of 101 patients were treated, including 73 patients who received the recommended dose regimen from baseline and 20 patients who had their dose switched to the recommended dose during the study. Of the 73 patients who received the recommended dose throughout treatment, baseline mean disease duration was 2.48 years and a JADAS-27 score of 22.73. At baseline, 84.9% of patients had received at least one conventional DMARD (mainly methotrexate), 13.7% received systemic glucocorticoids, and 19.2% had prior treatment with biological DMARDs (mainly TNF antagonists). The patients treated had subtypes of JIA that, at disease onset, included rheumatoid factor positive (17.8%), negative polyarticular JIA (65.8%), or extended oligoarticular JIA (16.4%).

Use of KEVZARA in pediatric patients with pJIA is supported by evidence from adequate and well-controlled studies of KEVZARA in adults with RA, pharmacokinetic data from adult patients with RA, and pharmacokinetic (PK) comparability from Study 4 [see Clinical Pharmacology (12.3)].

16 HOW SUPPLIED/STORAGE AND HANDLING

KEVZARA (sarilumab) injection is supplied as a clear and colorless to pale yellow solution in single-dose pre-filled syringes, and single-dose pre-filled pens.

Strength | Package Size | NDC Number
150 mg/1.14 mL | 2 syringes per pack | 0024-5908-01
200 mg/1.14 mL | 2 syringes per pack | 0024-5910-01

Strength | Package Size | NDC Number
150 mg/1.14 mL | 2 pre-filled pens per pack | 0024-5920-01
200 mg/1.14 mL | 2 pre-filled pens per pack | 0024-5922-01

Storage and Stability

Refrigerate at 36°F to 46°F (2°C to 8°C) in original carton to protect from light. Do not freeze. Do not shake.

If needed, patients/caregivers may store KEVZARA at room temperature up to 77°F (25°C) up to 14 days in the outer carton. Do not store above 77°F (25°C). After removal from the refrigerator, use KEVZARA within 14 days or discard.

17 PATIENT COUNSELING INFORMATION

Advise the patients to read the FDA-approved patient labeling (Medication Guide and Instructions for Use).

Infections

Inform patients that KEVZARA may lower their resistance to infections. Instruct patients to contact their physician immediately when symptoms suggesting infection appear, to ensure rapid evaluation and appropriate treatment [see Warning and Precautions (5.1)].

Gastrointestinal Perforation

Inform patients that some patients, particularly those also taking NSAIDS, and/or steroids, have had tears (perforations) of the stomach or intestines. Inform patients that gastrointestinal perforations have been reported in KEVZARA-treated patients in clinical studies, primarily as a complication of diverticulitis. Instruct patients to contact their physician immediately when symptoms of severe, persistent abdominal pain appear to ensure rapid evaluation and appropriate treatment.

Hypersensitivity and Serious Allergic Reaction

Assess patient suitability for home use for SC injection. Inform patients that some patients who have been treated with KEVZARA have developed serious allergic reactions. Advise patients to seek immediate medical attention if they experience any symptom of serious allergic reactions.

Instruction on Injection Technique

Instruct patients and caregivers to read the Instructions for Use before the patient starts using KEVZARA, and each time the patient gets a refill as there may be new information they need to know.

Provide guidance to patients and caregivers on proper subcutaneous injection technique, including aseptic technique, and how to use the pre-filled syringe or pre-filled pen correctly (see Instructions for Use).

The pre-filled syringe or pre-filled pen should be left at room temperature for 30 minutes or 60 minutes respectively (see the Instructions for Use) prior to use. The syringe or pen should be used within 14 days after being taken out of the refrigerator. A puncture-resistant container should be used to dispose the used pre-filled syringes or pre-filled pens and should be kept out of the reach of children. Instruct patients or caregivers in the technique as well as proper pre-filled syringe or pre-filled pen disposal, and caution against reuse of these items.

REGENERON
sanofi

Manufactured by:
sanofi-aventis U.S. LLC
Morristown, NJ 07960
A SANOFI COMPANY
U.S. License No. 1752

Marketed by:

sanofi-aventis U.S. LLC (Morristown, NJ 07960) and

Regeneron Pharmaceuticals, Inc. (Tarrytown, NY 10591)

For patent information: www.kevzara-patents.com

KEVZARA® is a registered trademark of Sanofi Biotechnology

©2025 Regeneron Pharmaceuticals, Inc. / sanofi-aventis U.S. LLC

MEDICATION GUIDE
KEVZARA® (KEV-za-ra)
(sarilumab)
injection, for subcutaneous use

What is the most important information I should know about KEVZARA?
KEVZARA can cause serious side effects including:

1. Serious Infections. KEVZARA is a prescription medicine that affects your immune system. KEVZARA can lower the ability of your immune system to fight infections. Some people have serious infections while using KEVZARA, including tuberculosis (TB), and infections caused by bacteria, fungi, or viruses that can spread throughout the body. Some people have died from these infections.
  Your healthcare provider should test you or your child for TB before starting KEVZARA.
  - Your healthcare provider should monitor you closely for signs and symptoms of TB during treatment with KEVZARA.
  You should not start using KEVZARA if you have any kind of infection unless your healthcare provider says it is okay.
  Before starting KEVZARA, tell your healthcare provider if you:
  - think you have an infection or have signs or symptoms of an infection, with or without a fever, such as:

- sweats or chills
- muscle aches
- cough
- shortness of breath
- blood in your phlegm

- weight loss
- warm, red or painful skin or sores on your body
- diarrhea or stomach pain
- burning when you urinate or urinating more often than normal
- feeling very tired

  - are being treated for an infection.
  - get a lot of infections or have infections that keep coming back.
  - have diabetes, HIV, or a weak immune system. People with these conditions have a higher chance of getting infections.
  - have TB, or have been in close contact with someone with TB.
  - live or have lived, or have traveled to certain parts of the country (such as the Ohio and Mississippi River valleys and the Southwest) where there is an increased chance of getting certain fungal infections (histoplasmosis, coccidioidomycosis, or blastomycosis). These infections may happen more often or become more severe if you use KEVZARA. Ask your healthcare provider if you do not know if you have lived in an area where these infections are common.
  - have or have had hepatitis.
  After starting KEVZARA, call your healthcare provider right away if you have any symptoms of an infection.
2. Changes in certain laboratory test results.
  Your or your child's healthcare provider should do blood tests before you start KEVZARA, 4 to 8 weeks after starting KEVZARA, and then every 3 months during treatment to check for:
  - low neutrophil count. Neutrophils are white blood cells that help the body fight off bacterial infections. A low neutrophil count is common with KEVZARA, and can be severe.
  - low platelet count. Platelets are blood cells that help with blood clotting and stop bleeding.
  - increase in certain liver function tests. An increase in certain liver function tests is common with KEVZARA, and can be severe.
  Your healthcare provider may not prescribe KEVZARA if your neutrophil or platelet counts are too low, or your liver function tests are too high. Your healthcare provider may stop your KEVZARA treatment for a period of time or change your dose if needed because of changes in these blood test results.
  Your or your child's healthcare provider should do blood tests 4 to 8 weeks after starting KEVZARA and then every 6 months during treatment to check for an:
  - increase in blood cholesterol levels.
3. Tears (perforation) of the stomach or intestines. Tell your healthcare provider if you have had a condition known as diverticulitis (inflammation in parts of the large intestine) or ulcers in your stomach or intestines. Some people using KEVZARA get tears in their stomach or intestine. This happens most often in people who also take nonsteroidal anti-inflammatory drugs (NSAIDs), corticosteroids, or methotrexate. Call your healthcare provider right away if you have fever and stomach (abdominal) pain that does not go away.
4. Cancer. KEVZARA may increase your risk of certain cancers by changing the way your immune system works. Tell your healthcare provider if you have ever had any type of cancer.

See "What are the possible side effects of KEVZARA?" for more information about side effects.

What is KEVZARA?
KEVZARA is an injectable prescription medicine called an interleukin-6 (IL-6) receptor blocker. KEVZARA is used:

- To treat adults with moderately to severely active rheumatoid arthritis (RA) after at least one other medicine called a disease modifying antirheumatic drug (DMARD) has been used and did not work well or could not be tolerated.
- To treat adults with polymyalgia rheumatica (PMR) after corticosteroids have been used and did not work well or when a slow decrease in the dose of corticosteroids (taper) cannot be tolerated.
- To treat people with active polyarticular juvenile idiopathic arthritis (pJIA) who weigh 63 kg or more.

It is not known if KEVZARA is safe and effective in children with pJIA under 2 years of age.

Who should not use KEVZARA?
Do not use KEVZARA if you or your child are allergic to sarilumab or any of the ingredients in KEVZARA. See the end of this Medication Guide for a complete list of ingredients in KEVZARA.

Before you or your child use KEVZARA, talk to your healthcare provider about all of your medical conditions, including if you or your child:

- have an infection. See "What is the most important information I should know about KEVZARA?"
- have liver problems.
- have had stomach (abdominal) pain or been diagnosed with diverticulitis or ulcers in your stomach or intestines.
- have recently received or are scheduled to receive a vaccine. People who take KEVZARA should not receive live vaccines.
  - All vaccines should be brought up-to-date before starting KEVZARA, unless urgent treatment initiation is required.
- plan to have surgery or a medical procedure.
- are pregnant or plan to become pregnant. It is not known if KEVZARA will harm your unborn baby.
- are breastfeeding or plan to breastfeed. It is not known if KEVZARA passes into your breast milk. Talk to your healthcare provider about the best way to feed your baby if you use KEVZARA.

Tell your healthcare provider about all the medicines you or your child take, including prescription and over-the-counter medicines, vitamins, and herbal supplements.
Especially tell your healthcare provider if you or your child use:

- any other medicines to treat your RA, PMR or pJIA. You should not take rituximab (Rituxan®), etanercept (Enbrel®), infliximab (Remicade®), anakinra (Kineret®), adalimumab (Humira®), abatacept (Orencia®), certolizumab (Cimzia®), golimumab (Simponi®), tocilizumab (Actemra®), or tofacitinib (Xeljanz®) while you are using KEVZARA. Using KEVZARA with these medicines may increase your risk of infection.
- medicines that affect the way certain liver enzymes work. Ask your healthcare provider if you are not sure if your medicine is one of these.

Know the medicines you take. Keep a list of them to show to your healthcare provider and pharmacist when you get a new medicine.

How should I use KEVZARA?

- See the detailed Instructions for Use that comes with this Medication Guide for instructions about the right way to prepare and give your KEVZARA injections at home.
- KEVZARA is given as an injection under the skin (subcutaneous injection).
- KEVZARA is available as a single-use pre-filled syringe and a single-use pre-filled pen. Your healthcare provider will prescribe the dose and type of KEVZARA that is best for you or your child.
- If your healthcare provider decides that you or a caregiver can give the injections of KEVZARA at home using the pre-filled pen or pre-filled syringe, you or your caregiver should receive training on the right way to prepare and inject KEVZARA. Do not try to inject KEVZARA until you have been shown the right way to give the injections by your healthcare provider.
- Inject 1 dose of KEVZARA every 2 weeks.

What are the possible side effects of KEVZARA?
KEVZARA can cause serious side effects, including:

- See "What is the most important information I should know about KEVZARA?"
- Serious allergic reactions. Serious allergic reactions can happen with KEVZARA. Get medical attention right away if you or your child have any of the following signs of a serious allergic reaction:

- shortness of breath or trouble breathing
- swelling of the lips, tongue, or face
- chest pain

- feeling dizzy or faint
- moderate or severe stomach (abdominal) pain or vomiting

Common side effects of KEVZARA include:

- injection site redness
- injection site itching
- upper respiratory tract infection
- urinary tract infection
- nasal congestion, sore throat, and runny nose

These are not all of the possible side effects of KEVZARA.
Call your doctor for medical advice about side effects. You may report side effects to FDA at 1-800-FDA-1088.
You may also report side effects to sanofi-aventis at 1-800-633-1610.

How should I store KEVZARA?

- Store KEVZARA in the refrigerator between 36°F to 46°F (2°C to 8°C). Store KEVZARA in the original carton until use to protect it from light.
- Do not freeze KEVZARA.
- Do not shake KEVZARA.
- KEVZARA may be stored at room temperature up to 77°F (25°C) for up to 14 days in the original outer carton.
- Throw away KEVZARA if it has been kept at room temperature and not been used within 14 days.

Keep KEVZARA and all medicines out of the reach of children.

General Information about the safe and effective use of KEVZARA.
Medicines are sometimes prescribed for purposes other than those listed in a Medication Guide. Do not use KEVZARA for a condition for which it was not prescribed. Do not give KEVZARA to other people, even if they have the same symptoms you have. It may harm them.
You can ask your healthcare provider or pharmacist for information about KEVZARA that is written for health professionals.

What are the ingredients in KEVZARA?
Active Ingredient: sarilumab
Inactive Ingredients: arginine, histidine, polysorbate 20, sucrose, and Water for Injection, USP.
REGENERON
sanofi
Manufactured by: sanofi-aventis U.S. LLC Morristown, NJ 07960, A SANOFI COMPANY U.S. License # 1752. Marketed by: sanofi-aventis U.S. LLC (Morristown, NJ 07960) and Regeneron Pharmaceuticals, Inc. (Tarrytown, NY 10591) KEVZARA® is a registered trademark of Sanofi Biotechnology ©2025 Regeneron Pharmaceuticals, Inc. / sanofi-aventis U.S. LLC
For more information, go to www.KEVZARA.com or call 1-844-KEVZARA (1-844-538-9272).

This Medication Guide has been approved by the U.S. Food and Drug Administration

Revised: May 2025

Instructions For Use KEVZARA® (KEV-za-ra) (sarilumab) injection, for subcutaneous use Single-dose Pre-filled Syringe (150 mg/1.14 mL)

Important information:

KEVZARA is available as a single-dose pre-filled syringe (called "syringe" in these instructions). The pre-filled syringe contains 150 mg of KEVZARA for injection under the skin (subcutaneous injection) 1 time every 2 weeks.

Do not try to inject KEVZARA until you have been shown the right way to give the injections by your healthcare provider.

Do | Do not
- Read all of the instructions carefully before using the syringe. - Keep unused syringes in the original carton and store in the refrigerator between 36°F and 46°F (2°C and 8°C). - Keep the carton in an insulated bag with an ice pack when traveling. - Let the syringe warm up at room temperature for at least 30 minutes before using. - Use the syringe within 14 days after taking it out of the refrigerator or insulated bag. - Keep the syringe and all medicines out of the reach of children. | - Do not use the syringe if it has been damaged or the needle cap is missing or not attached. Return the syringe and the package it came in to your pharmacy. - Do not remove the needle cap until just before you are ready to inject. - Do not touch the needle. - Do not re-use the syringe or try to put the cap back on the syringe. - Do not freeze or heat up the syringe. - Do not expose the syringe to direct sunlight. - Do not inject through your clothes.

Keep these instructions for future use.

If you have any further questions, ask your healthcare provider or call 1-844-KEVZARA (1-844-538-9272).

KEVZARA pre-filled syringe parts

What you will need for your injection:

- A new KEVZARA 150 mg/1.14 mL pre-filled syringe
- Alcohol wipe
- Cotton ball or gauze
- Sharps disposal container. See "How should I dispose of (throw away) KEVZARA pre-filled syringes?" at the end of this Instructions for Use.

Step A: Get ready for an injection

1. Prepare all of the equipment you will need on a clean, flat working surface.

- Take 1 syringe out of the package by holding the middle of the syringe body. Do not hold the syringe by the plunger, finger grip or needle cap. Do not pull off the needle cap until you are ready to inject.
- Keep the remaining syringe in the carton in the refrigerator.

2. Look at the label.

- Check that you have the correct medicine and the correct dose.
- Check the expiration date.
- Do not use the syringe if the expiration date has passed.

3. Look at the medicine.

- Check to see if the liquid in the syringe is clear and colorless to pale yellow.
- You may see air bubbles. This is normal.
- Do not inject if the liquid is cloudy, discolored or contains particles. Safely dispose of the syringe in a sharps container and get a new one.

4. Lay the syringe on a flat surface and allow it to warm up at room temperature for at least 30 minutes.

- Using the syringe at room temperature may make the injection more comfortable.
- Do not use the syringe if it has been out of the refrigerator for more than 14 days.
- Do not try to warm the syringe in any other way.

5. Select the injection site.

- You can inject into the front of your thigh or your belly (abdomen), but not the area 2 inches (5 cm) around your belly button (navel).
- If somebody else gives you the injection, you can also use the upper arm.
- Change the injection site each time you inject.
- Do not inject into skin that is tender, damaged or has bruises or scars.

6. Prepare the injection site.

- Wash your hands.
- Clean the skin at the injection site with an alcohol wipe and let it air dry before injecting.
- Do not touch the injection site again before the injection.

Step B: Give the injection

Complete Step B after completing all steps in Step A "Get ready for an injection".

1. Pull off the needle cap.

- Hold the syringe in the middle of the syringe body with the needle pointing away from you.
- Keep your hand away from the plunger.
- Do not get rid of any air bubbles in the syringe.
- Do not pull off the needle cap until you are ready to inject.
- Do not put the needle cap back on.

2. Pinch the skin.

- Use your thumb and first (index) finger to pinch a fold of skin at the cleaned injection site.

3. Insert the needle into the fold of skin at about a 45 degree angle.

4. Push the plunger down.

- Slowly push the plunger down as far as it will go until the syringe is empty.

5. Before you remove the needle, check that the syringe is empty.

- Pull the needle out at the same angle as inserted.
- If you see any blood at the injection site, press a cotton ball or gauze on the injection site.
- Do not rub the injection site.

6. Dispose of the syringe.

- The KEVZARA syringe should not be reused.
- Put the used syringe into your FDA-cleared sharps disposal container or a puncture resistant container (see "How should I dispose of (throw away) KEVZARA pre-filled syringes?").
- Do not put the needle cap back on.

How should I dispose of (throw away) KEVZARA pre-filled syringes?

- Put the used syringe in an FDA-cleared sharps disposal container right away after use. Do not throw away (dispose of) the syringe in your household trash.
- If you do not have an FDA-cleared sharps disposal container, you may use a household container that is:
  - made of a heavy-duty plastic,
  - can be closed with a tight-fitting, puncture-resistant lid, without sharps being able to come out,
  - upright and stable during use,
  - leak-resistant, and
  - properly labeled to warn of hazardous waste inside the container.
- When your sharps disposal container is almost full, you will need to follow your community guidelines for the right way to dispose of your sharps disposal container. There may be state or local laws about how you should throw away used needles and syringes. For more information about safe sharps disposal, and for specific information about sharps disposal in the state that you live in, go to the FDA's website at: http://www.fda.gov/safesharpsdisposal
- Do not reuse the syringe.
- Do not dispose of your used sharps disposal container in your household trash unless your community guidelines permit this. Do not recycle your used sharps disposal container.

Important: Always keep the sharps disposal container out of the reach of children.

This Instructions for Use has been approved by the U.S. Food and Drug Administration.

REGENERON
sanofi

Manufactured by:
sanofi-aventis U.S. LLC
Morristown, NJ 07960
A SANOFI COMPANY
U.S. License # 1752

Marketed by: sanofi-aventis U.S. LLC (Morristown, NJ 07960)
and Regeneron Pharmaceuticals, Inc. (Tarrytown, NY 10591)

KEVZARA® is a registered trademark of Sanofi Biotechnology
©2025 Regeneron Pharmaceuticals, Inc. / sanofi-aventis U.S. LLC

Issued: May 2025

Instructions For Use KEVZARA® (KEV-za-ra) (sarilumab) injection, for subcutaneous use Single-dose Pre-filled Syringe (200 mg/1.14 mL)

Important information:

KEVZARA is available as a single-dose pre-filled syringe (called "syringe" in these instructions). The pre-filled syringe contains 200 mg of KEVZARA for injection under the skin (subcutaneous injection) 1 time every 2 weeks.

Do not try to inject KEVZARA until you have been shown the right way to give the injections by your healthcare provider.

Do | Do not
- Read all of the instructions carefully before using the syringe. - Keep unused syringes in the original carton and store in the refrigerator between 36°F and 46°F (2°C and 8°C). - Keep the carton in an insulated bag with an ice pack when traveling. - Let the syringe warm up at room temperature for at least 30 minutes before using. - Use the syringe within 14 days after taking it out of the refrigerator or insulated bag. - Keep the syringe and all medicines out of the reach of children. | - Do not use the syringe if it has been damaged or the needle cap is missing or not attached. Return the syringe and the package it came in to your pharmacy. - Do not remove the needle cap until just before you are ready to inject. - Do not touch the needle. - Do not re-use the syringe or try to put the cap back on the syringe. - Do not freeze or heat up the syringe. - Do not expose the syringe to direct sunlight. - Do not inject through your clothes.

Keep these instructions for future use.

If you have any further questions, ask your healthcare provider or call 1-844-KEVZARA (1-844-538-9272).

KEVZARA pre-filled syringe parts

What you will need for your injection:

- A new KEVZARA 200 mg/1.14 mL pre-filled syringe
- Alcohol wipe
- Cotton ball or gauze
- Sharps disposal container. See "How should I dispose of (throw away) KEVZARA pre-filled syringes?" at the end of this Instructions for Use.

Step A: Get ready for an injection

1. Prepare all of the equipment you will need on a clean, flat working surface.

- Take 1 syringe out of the package by holding the middle of the syringe body. Do not hold the syringe by the plunger, finger grip or needle cap. Do not pull off the needle cap until you are ready to inject.
- Keep the remaining syringe in the carton in the refrigerator.

2. Look at the label.

- Check that you have the correct medicine and the correct dose.
- Check the expiration date.
- Do not use the syringe if the expiration date has passed.

3. Look at the medicine.

- Check to see if the liquid in the syringe is clear and colorless to pale yellow.
- You may see air bubbles. This is normal.
- Do not inject if the liquid is cloudy, discolored or contains particles. Safely dispose of the syringe in a sharps container and get a new one.

4. Lay the syringe on a flat surface and allow it to warm up at room temperature for at least 30 minutes.

- Using the syringe at room temperature may make the injection more comfortable.
- Do not use the syringe if it has been out of the refrigerator for more than 14 days.
- Do not try to warm the syringe in any other way.

5. Select the injection site.

- You can inject into the front of your thigh or your belly (abdomen), but not the area 2 inches (5 cm) around your belly button (navel).
- If somebody else gives you the injection, you can also use the upper arm.
- Change the injection site each time you inject.
- Do not inject into skin that is tender, damaged or has bruises or scars.

6. Prepare the injection site.

- Wash your hands.
- Clean the skin at the injection site with an alcohol wipe and let it air dry before injecting.
- Do not touch the injection site again before the injection.

Step B: Give the injection

Complete Step B after completing all steps in Step A "Get ready for an injection"

1. Pull off the needle cap.

- Hold the syringe in the middle of the syringe body with the needle pointing away from you.
- Keep your hand away from the plunger.
- Do not get rid of any air bubbles in the syringe.
- Do not pull off the needle cap until you are ready to inject.
- Do not put the needle cap back on.

2. Pinch the skin.

- Use your thumb and first (index) finger to pinch a fold of skin at the cleaned injection site.

3. Insert the needle into the fold of skin at about a 45 degree angle.

4. Push the plunger down.

- Slowly push the plunger down as far as it will go until the syringe is empty.

5. Before you remove the needle, check that the syringe is empty.

- Pull the needle out at the same angle as inserted.
- If you see any blood at the injection site, press a cotton ball or gauze on the site.
- Do not rub the injection site.

6. Dispose of the syringe.

- The KEVZARA syringe should not be reused.
- Put the used syringe into your FDA-cleared sharps disposal container of a puncture resistant container (see "How should I dispose of (throw away) KEVZARA pre-filled syringes?").
- Do not put the needle cap back on.

How should I dispose of (throw away) KEVZARA pre-filled syringes?

- Put the used syringe in an FDA-cleared sharps disposal container right away after use. Do not throw away (dispose of) the syringe in your household trash.
- If you do not have an FDA-cleared sharps disposal container, you may use a household container that is:
  - made of a heavy-duty plastic,
  - can be closed with a tight-fitting, puncture-resistant lid, without sharps being able to come out,
  - upright and stable during use,
  - leak-resistant, and
  - properly labeled to warn of hazardous waste inside the container.
- When your sharps disposal container is almost full, you will need to follow your community guidelines for the right way to dispose of your sharps disposal container. There may be state or local laws about how you should throw away used needles and syringes. For more information about safe sharps disposal, and for specific information about sharps disposal in the state that you live in, go to the FDA's website at: http://www.fda.gov/safesharpsdisposal
- Do not reuse the syringe.
- Do not dispose of your used sharps disposal container in your household trash unless your community guidelines permit this. Do not recycle your used sharps disposal container.

Important: Always keep the sharps disposal container out of the reach of children.

This Instructions for Use has been approved by the U.S. Food and Drug Administration.

REGENERON
sanofi

Manufactured by:
sanofi-aventis U.S. LLC
Morristown, NJ 07960
A SANOFI COMPANY
U.S. License # 1752

Marketed by: sanofi-aventis U.S. LLC, (Morristown, NJ 07960)
and Regeneron Pharmaceuticals, Inc. (Tarrytown, NY 10591)

KEVZARA® is a registered trademark of Sanofi Biotechnology
©2025 Regeneron Pharmaceuticals, Inc. / sanofi-aventis U.S. LLC

Issued: May 2025

Instructions For Use KEVZARA® (KEV-za-ra) (sarilumab) injection, for subcutaneous use Single-dose pre-filled pen (150 mg/1.14 mL)

Important information:

KEVZARA is available as a single-dose pre-filled pen (called "pen" in these instructions). The pre-filled pen contains 150 mg of KEVZARA for injection under the skin (subcutaneous injection) 1 time every 2 weeks.

Do not try to inject KEVZARA until you have been shown the right way to give the injections by your healthcare provider.

Do | Do not
- Read all of the instructions carefully before using the pre-filled pen. - Keep unused pens in the original carton and store in the refrigerator between 36°F and 46°F (2°C and 8°C). - Keep the carton in an insulated bag with an ice pack when traveling. - Let the pen warm up at room temperature for at least 60 minutes before using. - Use the pen within 14 days after taking it out of the refrigerator or insulated bag. - Keep the pen and all medicines out of the reach of children. | - Do not use the pre-filled pen if it has been damaged or the orange cap is missing or not attached. Return the pen and the package it came in to your pharmacy. - Do not remove the orange cap until just before you are ready to inject. - Do not touch the yellow needle cover. - Do not try to put the orange cap back on the pen. - Do not re-use the pen. - Do not freeze or heat up the pen. - Do not expose the pen to direct sunlight. - Do not inject through your clothes.

Keep these instructions for future use.

If you have any further questions, ask your healthcare provider or call 1-844-KEVZARA (1-844-538-9272).

KEVZARA pre-filled pen parts

What you will need for your injection:

- An unused KEVZARA 150 mg/1.14 mL pre-filled pen
- Alcohol wipe
- Cotton ball or gauze
- Sharps disposal container. See "How should I throw away (dispose of) KEVZARA pre-filled pens?" at the end of this Instructions for Use.

Step A: Get ready for an injection

1. Prepare all of the equipment you will need on a clean, flat working surface.

- Take 1 pen out of the packaging by holding the middle of the pen body. Do not remove the orange cap until you are ready to inject.
- Keep the remaining pen in the carton in the refrigerator.

2. Look at the label.

- Check that you have the correct medicine and the correct dose.
- Check the expiration date. This is shown on the side of the pen.
- Do not use the pen if the expiration date has passed.

3. Look at the window.

- Check to see that the liquid in the window is clear and colorless to pale yellow.
- You may see air bubbles. This is normal.
- Do not inject if the liquid is cloudy, discolored or contains particles. Safely throw away (dispose of) the pen in a sharps container and get a new one.
- The window is clear when the pen is unused. The window will turn solid yellow after the pen has been used.
- Do not use if the window is solid yellow. Safely dispose of the pen in a sharps container and get a new one.

4. Lay the pen on a flat surface and allow it to warm up at room temperature for at least 60 minutes.

- Using the pen at room temperature may make the injection more comfortable.
- Do not use the pen if it has been out of the refrigerator for more than 14 days.
- Do not try to warm the pen in any other way.

5. Select the injection site.

- You can inject into your thigh or belly (abdomen), but not the area 2 inches (5 cm) around your belly button (navel).
- If somebody else gives you the injection, you can also use the outer area of the upper arm.
- Change the injection site each time you inject.
- Do not inject into skin that is tender, damaged or has bruises or scars.

6. Prepare the injection site.

- Wash your hands.
- Clean the skin at the injection site with an alcohol wipe and let it air dry before injecting.
- Do not touch the injection site again before the injection.

Step B: Give the injection

Complete Step B after completing all steps in Step A "Get ready for an injection"

1. Twist or pull off the orange cap.

- Do not remove the orange cap until you are ready to inject.
- Do not touch the yellow needle cover.
- Do not put the orange cap back on.

2. Put the yellow needle cover on your skin at about a 90 degree angle.

- Make sure you can see the window.

3. Press down and hold the pen firmly against your skin.

- There will be a "click" when the injection starts.

4. Keep holding the pen firmly against your skin.

- The window will start to turn solid yellow.
- The injection can take up to 15 seconds.

5. There will be a second click when the injection is complete. Check to see if the entire window has turned solid yellow before you remove the pen.

- If you do not hear the second click, you should still check to see if the entire window has turned solid yellow.
- If the entire window does not turn solid yellow, this means that you may not have received your full dose of medicine. Call your healthcare provider right away.

6. Remove the pen from your skin.

- After you remove the pen from your skin, the needle will be covered automatically.
- If you see any blood at the injection site, press a cotton ball or gauze on the site.
- Do not rub the injection site.

7. Dispose of the pen

- The KEVZARA pre-filled pen should not be reused.
- Put the used pen into your FDA-cleared sharps disposal container or a puncture-resistant container (see "How should I throw away (dispose of) KEVZARA pre-filled pens?").
- Do not put the orange cap back on.

How should I throw away (dispose of) KEVZARA pre-filled pens?

- Put the used pen in an FDA-cleared sharps disposal container right away after use. Do not throw away (dispose of) the pen in your household trash.
- If you do not have an FDA-cleared sharps disposal container, you may use a household container that is:
  - made of a heavy-duty plastic,
  - can be closed with a tight-fitting, puncture-resistant lid, without sharps being able to come out,
  - upright and stable during use,
  - leak-resistant, and
  - properly labeled to warn of hazardous waste inside the container.
- When your sharps disposal container is almost full, you will need to follow your community guidelines for the right way to dispose of your sharps disposal container. There may be state or local laws about how you should throw away used needles and syringes. For more information about safe sharps disposal, and for specific information about sharps disposal in the state that you live in, go to the FDA's website at: http://www.fda.gov/safesharpsdisposal
- Do not reuse the pen.
- Do not dispose of your used sharps disposal container in your household trash unless your community guidelines permit this. Do not recycle your used sharps disposal container.

Important: Always keep the sharps disposal container out of the reach of children.

This Instructions for Use has been approved by the U.S. Food and Drug Administration.

REGENERON
sanofi

Manufactured by:
sanofi-aventis U.S. LLC
Morristown, NJ 07960
A SANOFI COMPANY
U.S. License # 1752

Marketed by: sanofi-aventis U.S. LLC (Morristown, NJ 07960)
and Regeneron Pharmaceuticals, Inc. (Tarrytown, NY 10591)

KEVZARA® is a registered trademark of Sanofi Biotechnology
©2025 Regeneron Pharmaceuticals, Inc. / sanofi-aventis U.S. LLC

Issued: May 2025

Instructions For Use KEVZARA® (KEV-za-ra) (sarilumab) injection, for subcutaneous use Single-dose pre-filled pen (200 mg/1.14 mL)

Important information:

KEVZARA is available as a single-dose pre-filled pen (called "pen" in these instructions). The pre-filled pen contains 200 mg of KEVZARA for injection under the skin (subcutaneous injection) 1 time every 2 weeks.

Do not try to inject KEVZARA until you have been shown the right way to give the injections by your healthcare provider.

Do | Do not
- Read all of the instructions carefully before using the pre-filled pen. - Keep unused pens in the original carton and store in the refrigerator between 36°F and 46°F (2°C and 8°C). - Keep the carton in an insulated bag with an ice pack when traveling. - Let the pen warm up at room temperature for at least 60 minutes before using. - Use the pen within 14 days after taking it out of the refrigerator or insulated bag. - Keep the pen and all medicines out of the reach of children. | - Do not use the pre-filled pen if it has been damaged or the orange cap is missing or not attached. Return the pen and the package it came in to your pharmacy. - Do not remove the orange cap until just before you are ready to inject. - Do not touch the yellow needle cover. - Do not try to put the orange cap back on the pen. - Do not re-use the pen. - Do not freeze or heat up the pen. - Do not expose the pen to direct sunlight. - Do not inject through your clothes.

Keep these instructions for future use.

If you have any further questions, ask your healthcare provider or call 1-844-KEVZARA (1-844-538-9272).

KEVZARA pre-filled pen parts

What you will need for your injection:

- An unused KEVZARA 200 mg/1.14 mL pre-filled pen
- Alcohol wipe
- Cotton ball or gauze
- Sharps disposal container. See "How should I throw away (dispose of) KEVZARA pre-filled pens?" at the end of this Instructions for Use.

Step A: Get ready for an injection

1. Prepare all of the equipment you will need on a clean, flat working surface.

- Take 1 pen out of the packaging by holding the middle of the pen body. Do not remove the orange cap until you are ready to inject.
- Keep the remaining pen in the carton in the refrigerator.

2. Look at the label.

- Check that you have the correct medicine and the correct dose.
- Check the expiration date. This is shown on the side of the pen.
- Do not use the pen if the expiration date has passed.

3. Look at the window.

- Check to see that the liquid in the window is clear and colorless to pale yellow.
- You may see air bubbles. This is normal.
- Do not inject if the liquid is cloudy, discolored or contains particles. Safely throw away (dispose of) the pen in a sharps container and get a new one.
- The window is clear when the pen is unused. The window will turn solid yellow after the pen has been used.
- Do not use if the window is solid yellow. Safely dispose of the pen in a sharps container and get a new one.

4. Lay the pen on a flat surface and allow it to warm up at room temperature for at least 60 minutes.

- Using the pen at room temperature may make the injection more comfortable.
- Do not use the pen if it has been out of the refrigerator for more than 14 days.
- Do not try to warm the pen in any other way.

5. Select the injection site.

- You can inject into your thigh or belly (abdomen), but not the area 2 inches (5 cm) around your belly button (navel).
- If somebody else gives you the injection, you can also use the outer area of the upper arm.
- Change the injection site each time you inject.
- Do not inject into skin that is tender, damaged or has bruises or scars.

6. Prepare the injection site.

- Wash your hands.
- Clean the skin at the injection site with an alcohol wipe and let it air dry before injecting.
- Do not touch the injection site again before the injection

Step B: Give the injection

Complete Step B after completing all steps in Step A "Get ready for an injection"

1. Twist or pull off the orange cap.

- Do not remove the orange cap until you are ready to inject.
- Do not touch the yellow needle cover.
- Do not put the orange cap back on.

2. Put the yellow needle cover on your skin at about a 90 degree angle.

- Make sure you can see the window.

3. Press down and hold the pen firmly against your skin.

- There will be a "click" when the injection starts.

4. Keep holding the pen firmly against your skin.

- The window will start to turn solid yellow.
- The injection can take up to 15 seconds.

5. There will be a second click when the injection is complete. Check to see if the entire window has turned solid yellow before you remove the pen.

- If you do not hear the second click, you should still check to see if the entire window has turned solid yellow.
- If the entire window does not turn solid yellow, this means that you may not have received your full dose of medicine. Call your healthcare provider right away.

6. Remove the pen from your skin.

- After you remove the pen from your skin, the needle will be covered automatically.
- If you see any blood at the injection site, press a cotton ball or gauze on the site.
- Do not rub the injection site.

7. Dispose of the pen

- The KEVZARA pre-filled pen should not be reused.
- Put the used pen into your FDA-cleared sharps disposal container or a puncture resistant container (see "How should I throw away (dispose of) KEVZARA pre-filled pens?").
- Do not put the orange cap back on.

How should I throw away (dispose of) KEVZARA pre-filled pens?

- Put the used pen in an FDA-cleared sharps disposal container right away after use. Do not throw away (dispose of) the pen in your household trash.
- If you do not have an FDA-cleared sharps disposal container, you may use a household container that is:
  - made of a heavy-duty plastic,
  - can be closed with a tight-fitting, puncture resistant lid, without sharps being able to come out,
  - upright and stable during use,
  - leak-resistant, and
  - properly labeled to warn of hazardous waste inside the container.
- When your sharps disposal container is almost full, you will need to follow your community guidelines for the right way to dispose of your sharps disposal container. There may be state or local laws about how you should throw away used needles and syringes. For more information about safe sharps disposal, and for specific information about sharps disposal in the state that you live in, go to the FDA's website at: http://www.fda.gov/safesharpsdisposal
- Do not reuse the pen.
- Do not dispose of your used sharps disposal container in your household trash unless your community guidelines permit this. Do not recycle your used sharps disposal container.

Important: Always keep the sharps disposal container out of the reach of children.

This Instructions for Use has been approved by the U.S. Food and Drug Administration.

REGENERON
sanofi

Manufactured by:
sanofi-aventis U.S. LLC
Morristown, NJ 07960
A SANOFI COMPANY
U.S. License # 1752

Marketed by: sanofi-aventis U.S. LLC (Morristown, NJ 07960)
and Regeneron Pharmaceuticals, Inc. (Tarrytown, NY 10591)

KEVZARA® is a registered trademark of Sanofi Biotechnology
©2025 Regeneron Pharmaceuticals, Inc. / sanofi-aventis U.S. LLC

Issued: May 2025

PRINCIPAL DISPLAY PANEL - 150 mg/1.14 mL Syringe Carton

NDC 0024-5908-01
Rx Only

KEVZARA®
(sarilumab)
injection

150 mg/1.14 mL (131.6 mg/mL)
2 Single-Dose Pre-filled Syringes
For Subcutaneous Injection Use Only

REGENERON
sanofi

Store in a refrigerator at 36°F to 46°F (2°C to 8°C) in the original
carton to protect from light. Do NOT freeze. Do NOT shake.

If needed, patients/caregivers may store KEVZARA at room
temperature up to 77°F (25°C) up to 14 days in the outer carton.
Do not store above 77°F (25°C). After removal from the
refrigerator, use KEVZARA within 14 days or discard.

Date removed from the refrigerator ____/____/____

ATTENTION: Enclosed Medication Guide is required for each patient

150 mg/1.14 mL

PRINCIPAL DISPLAY PANEL - 200 mg/1.14 mL Syringe Carton

NDC 0024-5910-01
Rx Only

KEVZARA®
(sarilumab)
injection

200 mg/1.14 mL (175.4 mg/mL)
2 Single-Dose Pre-filled Syringes
For Subcutaneous Injection Use Only

REGENERON
sanofi

Store in a refrigerator at 36°F to 46°F (2°C to 8°C) in the original
carton to protect from light. Do NOT freeze. Do NOT shake.

If needed, patients/caregivers may store KEVZARA at room
temperature up to 77°F (25°C) up to 14 days in the outer carton.
Do not store above 77°F (25°C). After removal from the
refrigerator, use KEVZARA within 14 days or discard.

Date removed from the refrigerator ____/____/____

ATTENTION: Enclosed Medication Guide is required for each patient

200 mg/1.14 mL

PRINCIPAL DISPLAY PANEL - 150 mg/1.14 mL Pen Carton

NDC 0024-5920-01
Rx Only

KEVZARA®
(sarilumab)
injection

150 mg/1.14 mL (131.6 mg/mL)
2 Single-Dose Pre-filled Pens
For Subcutaneous Injection Use Only

REGENERON
sanofi

Store in a refrigerator at 36°F to 46°F (2°C to 8°C) in the original
carton to protect from light. Do NOT freeze. Do NOT shake.

If needed, patients/caregivers may store KEVZARA at room
temperature up to 77°F (25°C) up to 14 days in the outer carton.
Do not store above 77°F (25°C). After removal from the
refrigerator, use KEVZARA within 14 days or discard.

Date removed from the refrigerator ____/____/____

ATTENTION: Enclosed Medication Guide is required for each patient

150 mg/1.14 mL

PRINCIPAL DISPLAY PANEL - 200 mg/1.14 mL Pen Carton

NDC 0024-5922-01
Rx Only

KEVZARA®
(sarilumab)
injection

200 mg/1.14 mL (175.4 mg/mL)
2 Single-Dose Pre-filled Pens
For Subcutaneous Injection Use Only

REGENERON
sanofi

Store in a refrigerator at 36°F to 46°F (2°C to 8°C) in the original
carton to protect from light. Do NOT freeze. Do NOT shake.

If needed, patients/caregivers may store KEVZARA at room
temperature up to 77°F (25°C) up to 14 days in the outer carton.
Do not store above 77°F (25°C). After removal from the
refrigerator, use KEVZARA within 14 days or discard.

Date removed from the refrigerator ____/____/____

ATTENTION: Enclosed Medication Guide is required for each patient

200 mg/1.14 mL